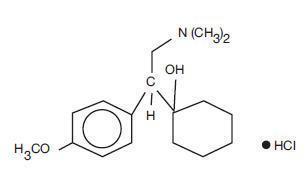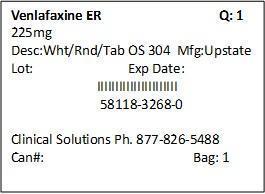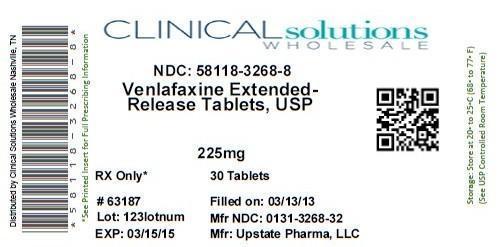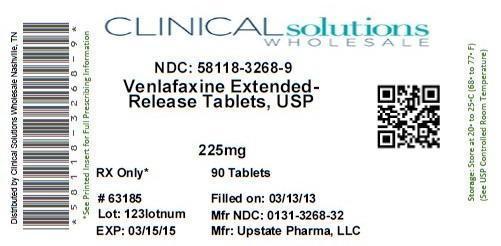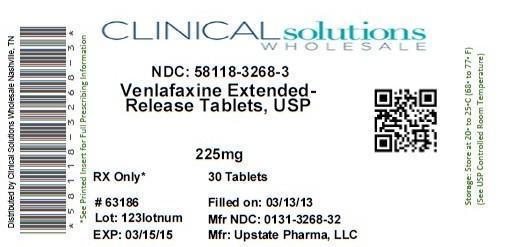 DRUG LABEL: Venlafaxine Hydrochloride
NDC: 58118-3268 | Form: TABLET, EXTENDED RELEASE
Manufacturer: Clinical Solutions Wholesale
Category: prescription | Type: HUMAN PRESCRIPTION DRUG LABEL
Date: 20130813

ACTIVE INGREDIENTS: venlafaxine hydrochloride 225 mg/1 1
INACTIVE INGREDIENTS: mannitol; povidone; cellulose, microcrystalline; POLYETHYLENE GLYCOL 1000; silicon dioxide; magnesium stearate; hypromelloses; lactose; titanium dioxide; triacetin; ferrosoferric oxide; propylene glycol

HIGHLIGHTS OF PRESCRIBING INFORMATION

These highlights do not include all the information needed to use Venlafaxine Extended Release Tablets safely and effectively. See full prescribing information for Venlafaxine Extended Release Tablets.
Venlafaxine Extended Release Tablets (venlafaxine hydrochloride) Extended Release Tablets for Oral use
Initial U.S. Approval: 1993

WARNING: SUICIDALITY AND ANTIDEPRESSANT DRUGS

WARNING: Suicidality and Antidepressants

See full prescribing information for complete boxed warning.

Increased risk of suicidal thinking and behavior in children, adolescents and young adults taking antidepressants for major depressive disorder (MDD) and other psychiatric disorders. Venlafaxine Extended Release Tablets are not approved for use in pediatric patients. (5.1)

RECENT MAJOR CHANGES

Warnings and Precautions, Serotonin Syndrome or Neuroleptic Malignant Syndrome (NMS)-like Reactions (5.3) | [01/2009]

1 INDICATIONS AND USAGE

Venlafaxine Extended Release Tablets are a selective serotonin and norepinephrine reuptake inhibitor (SNRI) indicated for:

- Major Depressive Disorder (MDD) (1.1)
- Social Anxiety Disorder (SAD) (1.2)

2 DOSAGE AND ADMINISTRATION

- Initial Treatment (2.1)
  Indication | Starting Dose | Dose Increase | Maximum Dose
  Major Depressive Disorder | 75 mg/day (in some patients, 37.5 mg/day for 4-7 days) | 75 mg/day increments at intervals of 4 days or longer | 225 mg/day
  Social Anxiety Disorder | 75 mg/day | No benefit at higher doses | 75 mg/day
- Venlafaxine extended-release tablets should be taken as a single daily dose with food in either the morning or evening at the same time each day. (2)
- Discontinuation: Gradual; individualized as necessary. (2.4)

3 DOSAGE FORMS AND STRENGTHS

- 37.5 mg, 75 mg, 150 mg, and 225 mg tablets (3)

4 CONTRAINDICATIONS

- Concomitant use of monoamine oxidase inhibitors (4)

5 WARNINGS AND PRECAUTIONS

- Suicidality: Monitor for clinical worsening and suicide risk. (5.1)
- Monoamine Oxidase Inhibitors (MAOIs): Serious interactions possible. Concomitant use contraindicated. Avoidance of MAOIs recommended for at least 14 days before starting venlafaxine. A MAOI should not be started within 7 days after stopping venlafaxine. (5.2)
- Serotonin Syndrome, or Neuroleptic Malignant Syndrome (NMS)-like reactions: Serotonin syndrome or NMS-like reactions have been reported with SSRIs and SNRIs. Discontinue Venlafaxine extended-release tablets and initiate supportive treatment. (5.3)
- Sustained hypertension may occur. Blood pressure monitoring recommended. (5.4)
- Mydriasis may occur. Patients with raised intraocular pressure or those at risk of acute narrow-angle glaucoma should be monitored. (5.5)
- Abrupt discontinuation or dose reduction: Discontinuation symptoms may occur (generally self-limiting; serious symptoms possible). Dose reduction recommended to be gradual. (5.6)
- Activation of Mania/Hypomania has occurred. (5.11)
- Symptomatic hyponatremia may occur. (5.12)
- Seizures have been reported. Use with caution in patients with seizure history. (5.13)
- Abnormal bleeding (most commonly ecchymosis) has been reported. (5.14)
- Serum cholesterol: Clinically relevant cholesterol increases may occur. Cholesterol measurements should be considered during long-term therapy. (5.15)
- Interstitial lung disease and eosinophilic pneumonia have been reported. (5.16)

6 ADVERSE REACTIONS

Major Depressive Disorder - Adverse events in short-term studies that occurred in at least 5% of the patients receiving venlafaxine extended-release capsules and at a rate at least twice that of the placebo group were abnormal ejaculation, gastrointestinal complaints (nausea, dry mouth, and anorexia), CNS complaints (dizziness, somnolence, and abnormal dreams), and sweating.

Social Anxiety Disorder - Adverse events in short-term studies that occurred in at least 5% of the patients receiving venlafaxine extended-release capsules and at a rate at least twice that of the placebo group were asthenia, gastrointestinal complaints (anorexia, dry mouth, nausea), CNS complaints (anxiety, insomnia, libido decreased, nervousness, somnolence, dizziness), abnormalities of sexual function (abnormal ejaculation, orgasmic dysfunction, impotence), yawn, sweating, and abnormal vision.

To report SUSPECTED ADVERSE REACTIONS, contact Upstate Pharma, LLC at 1-888-299-1053 or FDA at 1-800-FDA-1088 or www.fda.gov/medwatch.

7 DRUG INTERACTIONS

- MAOI's: concomitant use contraindicated (4). Avoid MAOI's 14 days before starting venlafaxine and 7 days after stopping venlafaxine (5.2).
- Cimetidine: Caution in patients with pre-existing hypertension, in elderly patients and patients with hepatic dysfunction. (7.2)
- Haloperidol: Increase in Haloperidol AUC and Cmax. (7.4)
- Ketoconazole: Increase in venlafaxine and O-desmethylvenlafaxine AUC and Cmax. Caution when using venlafaxine with substances that inhibit both CYP2D6 and CYP3A4. (7.7)
- Metoprolol: Possibly reduced blood-pressure lowering effect despite increased metoprolol plasma levels. Caution should be exercised with co-administration of venlafaxine and metoprolol. (7.8)
- CNS-active drugs: Caution when using venlafaxine with such drugs. (7.10)
- Serotonergic drugs (e.g., triptans, SSRIs, other SNRIs, linezolid, lithium, tramadol, or St. John's Wort): Potential for serotonin syndrome. Careful patient observation advised. (7.10)
- Tryptophan supplements: Concomitant use not recommended. (7.10)

8 USE IN SPECIFIC POPULATIONS

- Pregnancy: Use during pregnancy only if clearly needed. Neonates exposed to venlafaxine in the third trimester have developed complications requiring prolonged hospitalization, respiratory support, and tube feeding. Benefits and risk of venlafaxine use in the third trimester should be carefully considered. (2.3; 8.1)
- Nursing: Potential for serious adverse reactions in the infant. Discontinue nursing or drug, considering the importance of the drug to the mother. (8.3)
- Pediatric use: Not approved for use in pediatric patients. When considering use in a child or adolescent, balance potential risks with clinical need. (8.4)
- Hepatic impairment: Reduction of total daily dose by 50% recommended in patients with mild to moderate impairment. In patients with cirrhosis, further reduction may be necessary and dosing individualization may be desirable. (2.3; 8.6)
- Renal impairment: Reduction of daily dose by 25-50% recommended. Dosing individualization may be necessary. (2.3; 8.7)
- Hemodialysis: Reduction of daily dose by 50%. (2.3; 8.7)

FULL PRESCRIBING INFORMATION

Venlafaxine Extended Release Tablets (venlafaxine hydrochloride)

WARNING: SUICIDALITY AND ANTIDEPRESSANT DRUGS

Antidepressants increased the risk compared to placebo of suicidal thinking and behavior (suicidality) in children, adolescents, and young adults in short-term studies of Major Depressive Disorder (MDD) and other psychiatric disorders. Anyone considering the use of Venlafaxine Extended Release Tablets or any other antidepressant in a child, adolescent, or young adult must balance this risk with the clinical need. Short-term studies did not show an increase in the risk of suicidality with antidepressants compared to placebo in adults beyond age 24; there was a reduction in risk with antidepressants compared to placebo in adults aged 65 and older. Depression and certain other psychiatric disorders are themselves associated with increases in the risk of suicide. Patients of all ages who are started on antidepressant therapy should be monitored appropriately and observed closely for clinical worsening, suicidality, or unusual changes in behavior. Families and caregivers should be advised of the need for close observation and communication with the prescriber. Venlafaxine Extended Release Tablets are not approved for use in pediatric patients. [See Warnings and Precautions (5.1) and Patient Counseling Information (17.1)]

1 INDICATIONS AND USAGE

1.1 Major Depressive Disorder

Venlafaxine Extended Release Tablets (venlafaxine hydrochloride) are indicated for the treatment of major depressive disorder (MDD).

Efficacy of venlafaxine in MDD was shown in both short-term trials and a longer-term trial in MDD [see Clinical Studies (14.1)].

A major depressive episode (DSM-IV) implies a prominent and relatively persistent (nearly every day for at least 2 weeks) depressed mood or the loss of interest or pleasure in nearly all activities, representing a change from previous functioning, and includes the presence of at least five of the following nine symptoms during the same two-week period: depressed mood, markedly diminished interest or pleasure in usual activities, significant change in weight and/or appetite, insomnia or hypersomnia, psychomotor agitation or retardation, increased fatigue, feelings of guilt or worthlessness, slowed thinking or impaired concentration, a suicide attempt or suicidal ideation.

1.2 Social Anxiety Disorder

Venlafaxine Extended Release Tablets are indicated for the treatment of Social Anxiety Disorder (SAD), also known as Social Phobia, as defined in DSM-IV.

Social Anxiety Disorder (DSM-IV) is characterized by a marked and persistent fear of 1 or more social or performance situations in which the person is exposed to unfamiliar people or to possible scrutiny by others. Exposure to the feared situation almost invariably provokes anxiety, which may approach the intensity of a panic attack. The feared situations are avoided or endured with intense anxiety or distress. The avoidance, anxious anticipation, or distress in the feared situation(s) interferes significantly with the person's normal routine, occupational or academic functioning, or social activities or relationships, or there is a marked distress about having the phobias. Lesser degrees of performance anxiety or shyness generally do not require psychopharmacological treatment.

Efficacy of venlafaxine extended release in the treatment of SAD was established in short-term SAD trials [see Clinical Studies (14.2)].

2 DOSAGE AND ADMINISTRATION

Venlafaxine Extended Release Tablets should be administered in a single dose with food either in the morning or in the evening at approximately the same time each day. Each tablet should be swallowed whole with fluid and not divided, crushed, chewed, or placed in water.

2.1 Initial Treatment

Major Depressive Disorder

For most patients, the recommended starting dose for Venlafaxine Extended Release Tablets is 75 mg/day, administered in a single dose. In the clinical trials establishing the efficacy of venlafaxine hydrochloride extended-release capsules in moderately depressed outpatients, the initial dose of venlafaxine was 75 mg/day. For some patients, it may be desirable to start at 37.5 mg/day for 4 to 7 days, to allow new patients to adjust to the medication before increasing to 75 mg/day. While the relationship between dose and antidepressant response for venlafaxine hydrochloride extended-release capsules has not been adequately explored, patients not responding to the initial 75 mg/day dose may benefit from dose increases to a maximum of approximately 225 mg/day. Dose increases should be in increments of up to 75 mg/day, as needed, and should be made at intervals of not less than 4 days, since steady state plasma levels of venlafaxine and its major metabolites are achieved in most patients by day 4. In the clinical trials establishing efficacy, upward titration was permitted at intervals of 2 weeks or more; the average doses were about 140 to 180 mg/day [see Clinical Studies (14)].

It should be noted that, while the maximum recommended dose for moderately depressed outpatients is also 225 mg/day for venlafaxine hydrochloride immediate-release tablets, more severely depressed inpatients in one study of the development program for that product responded to a mean dose of 350 mg/day (range of 150 to 375 mg/day). Whether or not higher doses of Venlafaxine Extended Release Tablets are needed for more severely depressed patients is unknown; however, the experience with venlafaxine hydrochloride extended-release capsule doses higher than 225 mg/day is very limited. [See Warnings and Precautions (5.18)]

Social Anxiety Disorder (Social Phobia)

The recommended dose is 75 mg/day, administered in a single dose. There was no evidence that higher doses confer any additional benefit. [See Warnings and Precautions (5.18)]

2.2 Maintenance Treatment

There is no body of evidence available from controlled trials to indicate how long patients with major depressive disorder should be treated with Venlafaxine Extended Release Tablets.

It is generally agreed that acute episodes of major depressive disorder require several months or longer of sustained pharmacological therapy beyond response to the acute episode. In one study, in which patients responding during 8 weeks of acute treatment with venlafaxine hydrochloride extended-release capsules were assigned randomly to placebo or to the same dose of venlafaxine hydrochloride extended-release capsules (75, 150, or 225 mg/day, qAM) during 26 weeks of maintenance treatment as they had received during the acute stabilization phase, longer-term efficacy was demonstrated. A second longer-term study has demonstrated the efficacy of venlafaxine hydrochloride immediate-release tablets in maintaining a response in patients with recurrent major depressive disorder who had responded and continued to be improved during an initial 26 weeks of treatment and were then randomly assigned to placebo or venlafaxine hydrochloride immediate-release tablets for periods of up to 52 weeks on the same dose (100 to 200 mg/day, on a b.i.d. schedule)[see Clinical Studies (14)]. Based on these limited data, it is not known whether or not the dose of Venlafaxine Extended Release Tablets needed for maintenance treatment is identical to the dose needed to achieve an initial response. Patients should be periodically reassessed to determine the need for maintenance treatment and the appropriate dose for such treatment.

2.3 Special Populations

Treatment of Pregnant Women During the Third Trimester

Neonates exposed to venlafaxine hydrochloride extended-release capsules, other SNRIs, or SSRIs, late in the third trimester have developed complications requiring prolonged hospitalization, respiratory support, and tube feeding [see Use in Specific Populations (8.1)]. When treating pregnant women with Venlafaxine Extended Release Tablets during the third trimester, the physician should carefully consider the potential risks and benefits of treatment. The physician may consider tapering Venlafaxine Extended Release Tablets in the third trimester.

Patients with Hepatic Impairment

Given the decrease in clearance and increase in elimination half-life for both venlafaxine and ODV that is observed in patients with hepatic cirrhosis and mild and moderate hepatic impairment compared with normal subjects [see Use in Specific Populations (8.6) and Clinical Pharmacology (12.3)], it is recommended that the total daily dose be reduced by 50% in patients with mild to moderate hepatic impairment. Since there was much individual variability in clearance between patients with cirrhosis, it may be necessary to reduce the dose even more than 50%, and individualization of dosing may be desirable in some patients.

Patients with Renal Impairment

Given the decrease in clearance for venlafaxine and the increase in elimination half-life for both venlafaxine and ODV that is observed in patients with renal impairment (GFR = 10 to 70 mL/min) compared with normal subjects [see Use in Specific Populations (8.7) and Clinical Pharmacology (12.3)], it is recommended that the total daily dose be reduced by 25% to 50%.

In patients undergoing hemodialysis, it is recommended that the total daily dose be reduced by 50% . Because there was much individual variability in clearance between patients with renal impairment, individualization of dosage may be desirable in some patients.

Elderly Patients

No dose adjustment is recommended for elderly patients solely on the basis of age. As with any drug for the treatment of major depressive disorder or Social Anxiety Disorder, however, caution should be exercised in treating the elderly. When individualizing the dosage, extra care should be taken when increasing the dose.

2.4 Discontinuing Venlafaxine Extended Release Tablets

Symptoms associated with discontinuation of venlafaxine hydrochloride extended-release capsules, other SNRI's, and SSRI's have been reported [see Warnings and Precautions (5.6)]. Patients should be monitored for these symptoms when discontinuing treatment. A gradual reduction in the dose rather than abrupt cessation is recommended whenever possible. If intolerable symptoms occur following a decrease in the dose or upon discontinuation of treatment, then resuming the previously prescribed dose may be considered. Subsequently, the physician may continue decreasing the dose but at a more gradual rate. In clinical trials with venlafaxine hydrochloride extended-release capsules, tapering was achieved by reducing the daily dose by 75 mg at 1 week intervals. Individualization of tapering may be necessary.

2.5 Switching Patients from Venlafaxine Hydrochloride Immediate-Release Tablets

Depressed patients who are currently being treated at a therapeutic dose with venlafaxine hydrochloride immediate-release tablets may be switched to Venlafaxine Extended Release Tablets at the nearest equivalent dose (mg/day), e.g., 37.5 mg venlafaxine two-times-a-day to 75 mg Venlafaxine Extended Release Tablets once daily. However, individual dosage adjustments may be necessary.

2.6 Switching Patients To or From a Monoamine Oxidase Inhibitor

At least 14 days should elapse between discontinuation of an MAOI and initiation of therapy with Venlafaxine Extended Release Tablets. In addition, at least 7 days should be allowed after stopping Venlafaxine Extended Release Tablets before starting an MAOI [see Contraindications (4) and Warnings and Precautions (5.2)].

3 DOSAGE FORMS AND STRENGTHS

Venlafaxine Extended Release Tablets are available as:

- 37.5 mg tablets (round, biconvex, white coated tablets with OS301 printed on one side)
- 75 mg tablets (round, biconvex, white coated tablets with OS302 printed on one side)
- 150 mg tablets (round, biconvex, white coated tablets with OS303 printed on one side)
- 225 mg tablets (round, biconvex, white coated tablets with OS304 printed on one side)

4 CONTRAINDICATIONS

Concomitant use in patients taking monoamine oxidase inhibitors (MAOIs) is contraindicated [see Warnings and Precautions (5.2)].

5 WARNINGS AND PRECAUTIONS

5.1 Clinical Worsening and Suicide Risk

Patients with major depressive disorder (MDD), both adult and pediatric, may experience worsening of their depression and/or the emergence of suicidal ideation and behavior (suicidality) or unusual changes in behavior, whether or not they are taking antidepressant medications, and this risk may persist until significant remission occurs. Suicide is a known risk of depression and certain other psychiatric disorders, and these disorders themselves are the strongest predictors of suicide. There has been a long standing concern, however, that antidepressants may have a role in inducing worsening of depression and the emergence of suicidality in certain patients during the early phases of treatment. Pooled analyses of short-term placebo-controlled trials of antidepressant drugs (SSRIs and others) showed that these drugs increase the risk of suicidal thinking and behavior (suicidality) in children, adolescents, and young adults (ages 18-24) with major depressive disorder (MDD) and other psychiatric disorders. Short-term studies did not show an increase in the risk of suicidality with antidepressants compared to placebo in adults beyond age 24; there was a reduction with antidepressants compared to placebo in adults aged 65 and older.

The pooled analyses of placebo-controlled trials in children and adolescents with MDD, obsessive compulsive disorder (OCD), or other psychiatric disorders included a total of 24 short-term trials of 9 antidepressant drugs in over 4400 patients. The pooled analyses of placebo-controlled trials in adults with MDD or other psychiatric disorders included a total of 295 short-term trials (median duration of 2 months) of 11 antidepressant drugs in over 77,000 patients.

There was considerable variation in risk of suicidality among drugs, but a tendency toward an increase in the younger patients for almost all drugs studied. There were differences in absolute risk of suicidality across the different indications, with the highest incidence in MDD. The risk differences (drug vs placebo), however, were relatively stable within age strata and across indications. These risk differences (drug-placebo difference in the number of cases of suicidality per 1000 patients treated) are provided in Table 1

Table 1
Age Range | Drug-Placebo Difference in Number of Cases of Suicidality per 1000 Patients Treated
 | Increases Compared to Placebo
<18 | 14 additional cases
18-24 | 5 additional cases
 | Decreases Compared to Placebo
25-64 | 1 fewer case
≥65 | 6 fewer cases

No suicides occurred in any of the pediatric trials. There were suicides in the adult trials, but the number was not sufficient to reach any conclusion about drug effect on suicide.

It is unknown whether the suicidality risk extends to longer-term use, i.e., beyond several months. However, there is substantial evidence from placebo-controlled maintenance trials in adults with depression that the use of antidepressants can delay the recurrence of depression.

All patients being treated with antidepressants for any indication should be monitored appropriately and observed closely for clinical worsening, suicidality, and unusual changes in behavior, especially during the initial few months of a course of drug therapy, or at times of dose changes, either increases or decreases.

The following symptoms, anxiety, agitation, panic attacks, insomnia, irritability, hostility, aggressiveness, impulsivity, akathisia (psychomotor restlessness), hypomania, and mania, have been reported in adult and pediatric patients being treated with antidepressants for major depressive disorder as well as for other indications, both psychiatric and nonpsychiatric. Although a causal link between the emergence of such symptoms and either the worsening of depression and/or the emergence of suicidal impulses has not been established, there is concern that such symptoms may represent precursors to emerging suicidality.

Consideration should be given to changing the therapeutic regimen, including possibly discontinuing the medication, in patients whose depression is persistently worse, or who are experiencing emergent suicidality or symptoms that might be precursors to worsening depression or suicidality, especially if these symptoms are severe, abrupt in onset, or were not part of the patient's presenting symptoms.

If the decision has been made to discontinue treatment, medication should be tapered, as rapidly as is feasible, but with recognition that abrupt discontinuation can be associated with certain symptoms [see Dosage and Administration (2.5) and Warnings and Precautions (5.7)].

Families and caregivers of patients being treated with antidepressants for major depressive disorder or other indications, both psychiatric and nonpsychiatric, should be alerted about the need to monitor patients for the emergence of agitation, irritability, unusual changes in behavior, and the other symptoms described above, as well as the emergence of suicidality, and to report such symptoms immediately to health care providers. Such monitoring should include daily observation by families and caregivers. Prescriptions for Venlafaxine Extended Release Tablets should be written for the smallest quantity of tablets consistent with good patient management, in order to reduce the risk of overdose.

A major depressive episode may be the initial presentation of bipolar disorder. It is generally believed (though not established in controlled trials) that treating such an episode with an antidepressant alone may increase the likelihood of precipitation of a mixed/manic episode in patients at risk for bipolar disorder. Whether any of the symptoms described above represent such a conversion is unknown. However, prior to initiating treatment with an antidepressant, patients with depressive symptoms should be adequately screened to determine if they are at risk for bipolar disorder; such screening should include a detailed psychiatric history, including a family history of suicide, bipolar disorder, and depression. It should be noted that Venlafaxine Extended Release Tablets are not approved for use in treating bipolar depression.

5.2 Potential for Interaction with Monoamine Oxidase Inhibitors

Adverse reactions, some of which were serious, have been reported in patients who have recently been discontinued from a monoamine oxidase inhibitor (MAOI) and started on venlafaxine, or who have recently had venlafaxine therapy discontinued prior to initiation of an MAOI. These reactions have included tremor, myoclonus, diaphoresis, nausea, vomiting, flushing, dizziness, hyperthermia with features resembling neuroleptic malignant syndrome, seizures, and death. In patients receiving antidepressants with pharmacological properties similar to venlafaxine in combination with an MAOI, there have also been reports of serious, sometimes fatal, reactions. For a selective serotonin reuptake inhibitor, these reactions have included hyperthermia, rigidity, myoclonus, autonomic instability with possible rapid fluctuations of vital signs, and mental status changes that include extreme agitation progressing to delirium and coma. Some cases presented with features resembling neuroleptic malignant syndrome. Severe hyperthermia and seizures, sometimes fatal, have been reported in association with the combined use of tricyclic antidepressants and MAOIs. These reactions have also been reported in patients who have recently discontinued these drugs and have been started on an MAOI. The effects of combined use of venlafaxine and MAOIs have not been evaluated in humans or animals. Therefore, because venlafaxine is an inhibitor of both norepinephrine and serotonin reuptake, it is recommended that Venlafaxine Extended Release Tablets (venlafaxine hydrochloride) not be used in combination with an MAOI, or within at least 14 days of discontinuing treatment with an MAOI. Based on the half-life of venlafaxine, at least 7 days should be allowed after stopping venlafaxine before starting an MAOI.

5.3 Serotonin Syndrome or Neuroleptic Malignant Syndrome (NMS)-like Reactions

The development of a potentially life-threatening serotonin syndrome or Neuroleptic Malignant Syndrome (NMS)-like reactions have been reported with SNRIs and SSRIs alone, including Venlafaxine Extended Release Tablets treatment, but particularly with concomitant use of serotonergic drugs (including triptans), with drugs which impair metabolism of serotonin (including MAOIs), or with antipsychotics or other dopamine antagonists. Serotonin syndrome symptoms may include mental status changes (e.g., agitation, hallucinations, coma), autonomic instability (e.g., tachycardia, labile blood pressure, hyperthermia), neuromuscular aberrations (e.g., hyperreflexia, incoordination) and/or gastrointestinal symptoms (e.g., nausea, vomiting, diarrhea) [see Drug Interactions (7.10)]. Serotonin syndrome, in its most severe form can resemble neuroleptic malignant syndrome, which includes hyperthermia, muscle rigidity, autonomic instability with possible rapid fluctuation of vital signs, and mental status changes. Patients should be monitored for the emergence of serotonin syndrome or NMS-like signs and symptoms.

The concomitant use of Venlafaxine Extended Release Tablets with MAOIs intended to treat depression is contraindicated [see Contraindications (4) and Warnings and Precautions (5.2)]. If concomitant treatment of Venlafaxine Extended Release Tablets with a 5-hydroxytryptamine receptor agonist (triptan) is clinically warranted, careful observation of the patient is advised, particularly during treatment initiation and dose increases [see Drug Interactions (7.10)].

The concomitant use of Venlafaxine Extended Release Tablets with serotonin precursors (such as tryptophan) is not recommended [see Drug Interactions (7.10)]. Treatment with Venlafaxine Extended Release Tablets and any concomitant serotonergic or antidopaminergic agents, including antipsychotics, should be discontinued immediately if the above events occur and supportive symptomatic treatment should be initiated.

5.4 Sustained Hypertension

Venlafaxine hydrochloride extended-release capsule treatment is associated with sustained hypertension (defined as treatment-emergent supine diastolic blood pressure (SDBP) ≥90 mm Hg and ≥10 mm Hg above baseline for 3 consecutive on-therapy visits) (see Table 2).

An analysis for patients in venlafaxine hydrochloride immediate-release tablet studies meeting criteria for sustained hypertension revealed a dose-dependent increase in the incidence of sustained hypertension for immediate-release venlafaxine hydrochloride (see Table 3).

An insufficient number of patients received mean doses of venlafaxine hydrochloride extended-release capsules over 300 mg/day to fully evaluate the incidence of sustained increases in blood pressure at these higher doses.

Table 2: Number (%) of Sustained Elevations in SDBP in Venlafaxine Hydrochloride Extended-Release Capsule Premarketing Studies by Indication
Major Depressive Disorder (75-375 mg/day) | Other Clinical Trials (75-225 mg/day)
19/705 (3) | 5/771 (0.6)

Table 3: Incidence (%) of Sustained Elevations in SDBP in Venlafaxine Hydrochloride Immediate-Release Tablet Studies
Venlafaxine mg/day | Incidence
<100 | 3%
>100 to ≤200 | 5%
>200 to ≤300 | 7%
>300 | 13%

In premarketing major depressive disorder studies, 0.7% (5/705) of the venlafaxine hydrochloride extended-release capsule-treated patients discontinued treatment because of elevated blood pressure. Among these patients, most of the blood pressure increases were in a modest range (12 to 16 mm Hg, SDBP). In other clinical studies, 0.6% (5/771) of the venlafaxine hydrochloride extended-release capsule-treated patients discontinued treatment because of elevated blood pressure. In these patients, the blood pressure increases were modest (1 to 24 mm Hg, SDBP).

Sustained increases of SDBP could have adverse consequences. Cases of elevated blood pressure requiring immediate treatment have been reported in post marketing experience. Pre-existing hypertension should be controlled before treatment with venlafaxine. It is recommended that patients receiving venlafaxine hydrochloride extended-release tablets have regular monitoring of blood pressure. For patients who experience a sustained increase in blood pressure while receiving venlafaxine, either dose reduction or discontinuation should be considered.

Elevations in Systolic and Diastolic Blood Pressure

In placebo-controlled premarketing studies, there were changes in mean blood pressure (see Table 4 for mean change in supine systolic and supine diastolic blood pressure). Across most indications, a dose-related increase in supine systolic and diastolic blood pressure was evident in venlafaxine hydrochloride extended-release capsule-treated patients.

Table 4: Final On-Therapy Mean Changes from Baseline in Supine Systolic and Diastolic Blood Pressure (mm Hg) Results by Indication, Study Duration, and Dose in Placebo-Controlled Trials
 | Venlafaxine Hydrochloride Extended-Release Capsules mg/day |  |  |  | Placebo
 | ≤75 |  | >75
 | SSBP [Supine Systolic Blood Pressure] | SDBP [Supine Diastolic Blood Pressure] | SSBP | SDBP | SSBP | SDBP
Major Depressive Disorder 8-12 weeks | -0.28 | 0.37 | 2.93 | 3.56 | -1.08 | -0.10
Other Clinical Trials 12 weeks | -0.29 | -1.26 | 1.18 | 1.34 | -1.96 | -1.22

Across all clinical trials, 1.4% of patients in the venlafaxine hydrochloride extended-release capsule-treated groups experienced a ≥15 mm Hg increase in supine diastolic blood pressure with blood pressure ≥105 mm Hg compared to 0.9% of patients in the placebo groups. Similarly, 1% of patients in the venlafaxine hydrochloride extended-release capsule-treated groups experienced a ≥20 mm Hg increase in supine systolic blood pressure with blood pressure ≥180 mm Hg compared to 0.3% of patients in the placebo groups.

5.5 Mydriasis

Mydriasis has been reported in association with venlafaxine; therefore patients with raised intraocular pressure or those at risk of acute narrow-angle glaucoma (angle-closure glaucoma) should be monitored [see Patient Counseling Information (17.8)].

5.6 Discontinuation of Treatment with Venlafaxine Extended Release Tablets

Discontinuation symptoms have been systematically evaluated in patients taking venlafaxine, to include prospective analyses of clinical trials and retrospective surveys of trials in major depressive disorder and social anxiety disorder. Abrupt discontinuation or dose reduction of venlafaxine at various doses has been found to be associated with the appearance of new symptoms, the frequency of which increased with increased dose level and with longer duration of treatment. Reported symptoms include agitation, anorexia, anxiety, confusion, impaired coordination and balance, diarrhea, dizziness, dry mouth, dysphoric mood, fasciculation, fatigue, headaches, hypomania, insomnia, nausea, nervousness, nightmares, sensory disturbances (including shock-like electrical sensations), somnolence, sweating, tremor, vertigo, and vomiting.

During marketing of venlafaxine hydrochloride extended-release capsules, other SNRI's (Serotonin and Norepinephrine Reuptake Inhibitors), and SSRI's (Selective Serotonin Reuptake Inhibitors), there have been spontaneous reports of adverse reactions occurring upon discontinuation of these drugs, particularly when abrupt, including the following: dysphoric mood, irritability, agitation, dizziness, sensory disturbances (e.g. paresthesias such as electric shock sensations), anxiety, confusion, headache, lethargy, emotional lability, insomnia, hypomania, tinnitus, and seizures. While these reactions are generally self-limiting, there have been reports of serious discontinuation symptoms.

Patients should be monitored for these symptoms when discontinuing treatment with Venlafaxine Extended Release Tablets. A gradual reduction in the dose rather than abrupt cessation is recommended whenever possible. If intolerable symptoms occur following a decrease in the dose or upon discontinuation of treatment, then resuming the previously prescribed dose may be considered. Subsequently, the physician may continue decreasing the dose but at a more gradual rate [see Dosage and Administration (2.4)].

5.7 Insomnia and Nervousness

Treatment-emergent insomnia and nervousness were more commonly reported for patients treated with venlafaxine hydrochloride extended-release capsules than with placebo in pooled analyses of short-term major depressive disorder and other clinical studies, as shown in Table 5.

Table 5 Incidence of Insomnia and Nervousness in Placebo-Controlled Major Depressive Disorder and Other Trials
 | Major Depressive Disorder |  | Other Trials
 | Venlafaxine Hydrochloride Extended-Release Capsules | Placebo | Venlafaxine Hydrochloride Extended-Release Capsules | Placebo
Symptom | n = 357 | n = 285 | N = 819 | n = 695
Insomnia | 17% | 11% | 24% | 8%
Nervousness | 10% | 5% | 10% | 5%

Insomnia and nervousness each led to drug discontinuation in 0.9% of the patients treated with venlafaxine hydrochloride extended-release capsules in major depressive disorder studies.

In other clinical trials, insomnia and nervousness led to drug discontinuation in 2% and 1%, respectively, of the patients treated with venlafaxine hydrochloride extended-release capsules up to 12 weeks.

5.8 Changes in Weight

Adult Patients: A loss of 5% or more of body weight occurred in 7% of patients treated with venlafaxine hydrochloride extended-release capsules and 2% of placebo-treated patients in the short-term placebo-controlled major depressive disorder trials. The discontinuation rate for weight loss associated with venlafaxine hydrochloride extended-release capsules was 0.1% in major depressive disorder studies. In other placebo-controlled trials, 4% of the patients treated with venlafaxine hydrochloride extended-release capsules and 1% of the placebo-treated patients sustained a loss of 7% or more of body weight during up to 6 months of treatment. None of the patients receiving venlafaxine hydrochloride extended-release capsules in other studies discontinued for weight loss.

The safety and efficacy of venlafaxine therapy in combination with weight loss agents, including phentermine, have not been established. Co-administration of Venlafaxine Extended Release Tablets and weight loss agents is not recommended. Venlafaxine Extended Release Tablets are not indicated for weight loss alone or in combination with other products.

Pediatric Patients: Weight loss has been observed in pediatric patients (ages 6-17) receiving venlafaxine hydrochloride extended-release capsules. In a pooled analysis of four eight-week, double-blind, placebo-controlled, flexible dose outpatient trials for major depressive disorder (MDD) and another disorder, patients treated with venlafaxine hydrochloride extended-release capsules lost an average of 0.45 kg (n = 333), while placebo-treated patients gained an average of 0.77 kg (n = 333). More patients treated with venlafaxine hydrochloride extended-release capsules than with placebo experienced a weight loss of at least 3.5% in the studies (18% of patients treated with venlafaxine hydrochloride extended-release capsules vs. 3.6% of placebo-treated patients; p<0.001). In a 16-week, double-blind, placebo-controlled, flexible dose outpatient study for another disorder, venlafaxine hydrochloride extended-release capsule-treated patients lost an average of 0.75 kg (n=137), while placebo-treated patients gained an average of 0.76 kg (n=148). More patients treated with venlafaxine hydrochloride extended-release capsules than with placebo experienced a weight loss of at least 3.5% in the study (47% of patients treated with venlafaxine hydrochloride extended-release capsules vs. 14% of placebo-treated patients; p<0.001). Weight loss was not limited to patients with treatment-emergent anorexia [see Warnings and Precautions (5.10)].

The risks associated with longer-term use of venlafaxine hydrochloride extended-release capsules were assessed in an open-label MDD study of children and adolescents who received venlafaxine hydrochloride extended-release capsules for up to six months. The children and adolescents in the study had increases in weight that were less than expected based on data from age- and sex-matched peers. The difference between observed weight gain and expected weight gain was larger for children (<12 years old) than for adolescents (≥12 years old).

5.9 Changes in Height

Pediatric Patients: During an eight-week, placebo-controlled non-MDD study, venlafaxine hydrochloride extended-release capsule-treated patients (ages 6-17) grew an average of 0.3 cm (n=122), while placebo-treated patients grew an average of 1.0 cm (n=132); p=0.041. This difference in height increase was most notable in patients younger than twelve. During the eight-week placebo-controlled MDD studies, venlafaxine hydrochloride extended-release capsule-treated patients grew an average of 0.8 cm (n = 146), while placebo-treated patients grew an average of 0.7 cm (n = 147). During a 16-week, placebo-controlled non-MDD study, both the venlafaxine hydrochloride extended-release capsule-treated patients (n=109) and the placebo-treated (n=112) patients each grew an average of 1.0 cm. In the six-month, open-label MDD study, children and adolescents had height increases that were less than expected based on data from age- and sex-matched peers. The difference between observed growth rates and expected growth rates was larger for children (<12 years old) than for adolescents (≥12 years old).

5.10 Changes in Appetite

Adult Patients: Treatment-emergent anorexia was more commonly reported for patients treated with venlafaxine hydrochloride extended-release capsules (8%) than for placebo-treated patients (4%) in the pool of short-term, double-blind, placebo-controlled major depressive disorder studies. The discontinuation rate for anorexia associated with venlafaxine hydrochloride extended-release capsules was 1.0% in major depressive disorder studies. Treatment-emergent anorexia was more commonly reported for patients treated with venlafaxine hydrochloride extended-release capsules (20%) than for placebo-treated patients (2%) in the pool of short-term, double-blind, placebo-controlled Social Anxiety Disorder studies. The discontinuation rate for anorexia was 0.4% for patients receiving venlafaxine hydrochloride extended-release capsules for up to 12 weeks in Social Anxiety Disorder studies.

Pediatric Patients: Decreased appetite has been observed in pediatric patients receiving venlafaxine hydrochloride extended-release capsules. In placebo-controlled trials in MDD and another disorder, 10% of patients aged 6-17 treated with venlafaxine hydrochloride extended-release capsules for up to eight weeks and 3% of patients treated with placebo reported treatment-emergent anorexia (decreased appetite). None of the patients receiving venlafaxine hydrochloride extended-release capsules discontinued for anorexia or weight loss. In a placebo-controlled non-MDD trial, 22% and 3% of patients aged 8-17 treated for up to 16 weeks with venlafaxine hydrochloride extended-release capsules and placebo, respectively, reported treatment-emergent anorexia (decreased appetite). The discontinuation rates for anorexia were 0.7% and 0.0% for patients receiving venlafaxine hydrochloride extended-release capsules and placebo, respectively; the discontinuation rates for weight loss were 0.7% for patients receiving either venlafaxine hydrochloride extended-release capsules or placebo.

5.11 Activation of Mania/Hypomania

During premarketing major depressive disorder studies, mania or hypomania occurred in 0.3% of patients treated with venlafaxine hydrochloride extended-release capsules and 0.0% placebo patients. In premarketing Social Anxiety Disorder studies, no patients treated with venlafaxine hydrochloride extended-release capsules and no placebo-treated patients experienced mania or hypomania. In all premarketing major depressive disorder trials with venlafaxine hydrochloride immediate-release tablets, mania or hypomania occurred in 0.5% of venlafaxine-treated patients compared with 0% of placebo patients. Mania/hypomania has also been reported in a small proportion of patients with mood disorders who were treated with other marketed drugs to treat major depressive disorder. As with all drugs effective in the treatment of major depressive disorder, Venlafaxine Extended Release Tablets should be used cautiously in patients with a history of mania.

5.12 Hyponatremia

Hyponatremia may occur as a result of treatment with SSRI's and SNRI's, including Venlafaxine Extended Release Tablets. In many cases, this hyponatremia appears to be the result of the syndrome of inappropriate antidiuretic hormone secretion (SIADH). Cases with serum sodium lower than 110 mmol/L have been reported. Elderly patients may be at greater risk of developing hyponatremia with SSRIs and SNRIs. Also, patients taking diuretics or who are otherwise volume depleted may be at greater risk [see Use in Specific Populations (8.5)]. Discontinuation of Venlafaxine Extended Release Tablets should be considered in patients with symptomatic hyponatremia and appropriate medical intervention should be instituted.

Signs and symptoms of hyponatremia include headache, difficulty concentrating, memory impairment, confusion, weakness, and unsteadiness, which may lead to falls. Signs and symptoms associated with more severe and/or acute cases have included hallucination, syncope, seizure, coma, respiratory arrest, and death.

5.13 Seizures

During premarketing experience, no seizures occurred among 705 patients treated with venlafaxine hydrochloride extended-release capsules in the major depressive disorder studies or among 277 patients treated with venlafaxine hydrochloride extended-release capsules in Social Anxiety Disorder studies. In all premarketing major depressive disorder trials with venlafaxine hydrochloride immediate-release tablets, seizures were reported at various doses in 0.3% (8/3082) of venlafaxine-treated patients. Venlafaxine Extended Release Tablets, like many antidepressants, should be used cautiously in patients with a history of seizures and should be discontinued in any patient who develops seizures.

5.14 Abnormal Bleeding

SSRIs and SNRIs, including Venlafaxine Extended Release Tablets, may increase the risk of bleeding events. Concomitant use of aspirin, nonsteroidal anti-inflammatory drugs, warfarin, and other anticoagulants may add to this risk. Case reports and epidemiological studies (case-control and cohort design) have demonstrated an association between use of drugs that interfere with serotonin reuptake and the occurrence of gastrointestinal bleeding. Bleeding events related to SSRIs and SNRIs use have ranged from ecchymoses, hematomas, epistaxis, and petechiae to life-threatening hemorrhages.

Patients should be cautioned about the risk of bleeding associated with the concomitant use of Venlafaxine Extended Release Tablets and NSAIDs, aspirin, or other drugs that affect coagulation.

5.15 Serum Cholesterol Elevation

Clinically relevant increases in serum cholesterol were recorded in 5.3% of venlafaxine-treated patients and 0.0% of placebo-treated patients treated for at least 3 months in placebo-controlled trials [see Adverse Reactions (6.1)]. Measurement of serum cholesterol levels should be considered during long-term treatment.

5.16 Interstitial Lung Disease and Eosinophilic Pneumonia

Interstitial lung disease and eosinophilic pneumonia associated with venlafaxine therapy have been rarely reported. The possibility of these adverse reactions should be considered in venlafaxine-treated patients who present with progressive dyspnea, cough or chest discomfort. Such patients should undergo a prompt medical evaluation, and discontinuation of venlafaxine therapy should be considered.

5.17 Use in Patients With Heart Disease

Premarketing experience with venlafaxine in patients with concomitant systemic illness is limited. Caution is advised in administering Venlafaxine Extended Release Tablets to patients with diseases or conditions that could affect hemodynamic responses.

Venlafaxine has not been evaluated or used to any appreciable extent in patients with a recent history of myocardial infarction or unstable heart disease. Patients with these diagnoses were systematically excluded from many clinical studies during venlafaxine's premarketing testing. The electrocardiograms were analyzed for 275 patients who received venlafaxine hydrochloride extended-release capsules and 220 patients who received placebo in 8- to 12-week double-blind, placebo-controlled trials in major depressive disorder as well as for 195 patients who received venlafaxine hydrochloride extended-release capsules and 228 patients who received placebo in 12-week double-blind, placebo-controlled trials in Social Anxiety Disorder. The mean change from baseline in corrected QT interval (QTc) for patients treated with venlafaxine hydrochloride extended-release capsules in major depressive disorder studies was increased relative to that for placebo-treated patients (increase of 4.7 msec for venlafaxine hydrochloride extended-release capsules and decrease of 1.9 msec for placebo). The mean change from baseline in QTc for patients treated with venlafaxine hydrochloride extended-release capsules in the Social Anxiety Disorder studies was increased relative to that for placebo-treated patients (increase of 2.8 msec for venlafaxine hydrochloride extended-release capsules and decrease of 2.0 msec for placebo).

In these same trials, the mean change from baseline in heart rate for patients treated with venlafaxine hydrochloride extended-release capsules in the major depressive disorder studies was significantly higher than that for placebo (a mean increase of 4 beats per minute for venlafaxine hydrochloride extended-release capsules and 1 beat per minute for placebo). The mean change from baseline in heart rate for patients treated with venlafaxine hydrochloride extended-release capsules in the Social Anxiety Disorder studies was significantly higher than that for placebo (a mean increase of 5 beats per minute for venlafaxine hydrochloride extended-release capsules and no change for placebo).

In a flexible-dose study, with doses of venlafaxine hydrochloride immediate-release tablets in the range of 200 to 375 mg/day and mean dose greater than 300 mg/day, patients treated with venlafaxine hydrochloride immediate-release tablets had a mean increase in heart rate of 8.5 beats per minute compared with 1.7 beats per minute in the placebo group.

As increases in heart rate were observed, caution should be exercised in patients whose underlying medical conditions might be compromised by increases in heart rate (e.g., patients with hyperthyroidism, heart failure, or recent myocardial infarction).

Evaluation of the electrocardiograms for 769 patients who received venlafaxine hydrochloride immediate-release tablets in 4- to 6-week double-blind, placebo-controlled trials showed that the incidence of trial-emergent conduction abnormalities did not differ from that with placebo.

5.18 Laboratory Tests

There are no specific laboratory tests recommended.

6 ADVERSE REACTIONS

6.1 Clinical Studies Experience

Data Sources

The information included in subsection "Adverse Findings Observed in Short-Term, Placebo-Controlled Studies with Venlafaxine Hydrochloride Extended-Release Capsules" is based on data from a pool of three 8- and 12-week controlled clinical trials in major depressive disorder (includes two U.S. trials and one European trial), and on data up to 12 weeks from a pool of two controlled clinical trials in Social Anxiety Disorder. Information on additional adverse reactions associated with venlafaxine hydrochloride extended-release capsules in the entire development program for the formulation and with venlafaxine hydrochloride immediate-release tablets is included in the subsection "Other Adverse Reactions Observed During the Premarketing Evaluation of Venlafaxine Hydrochloride Immediate-Release Tablets and Venlafaxine Hydrochloride Extended-Release Capsules" [see also Warnings and Precautions (5)].

Because clinical trials are conducted under widely varying conditions, adverse reaction rates observed in the clinical trials of a drug cannot be directly compared to rates in the clinical trials of another drug and may not reflect the rates observed in practice.

Adverse Findings Observed in Short-Term, Placebo-Controlled Studies with Venlafaxine Hydrochloride Extended-Release Capsules

Adverse Reactions Associated with Discontinuation of Treatment

Major Depressive Disorder: Approximately 11% of the 357 patients who received venlafaxine hydrochloride extended-release capsules in placebo-controlled clinical trials for major depressive disorder discontinued treatment due to an adverse reaction, compared with 6% of the 285 placebo-treated patients in those studies. Adverse reactions that led to treatment discontinuation in a least 2% of drug-treated patients were nausea, dizziness, and somnolence.

Social Anxiety Disorder: Approximately 17% of the 277 patients who received venlafaxine hydrochloride extended-release capsules in placebo-controlled clinical trials for Social Anxiety Disorder discontinued treatment due to an adverse reaction, compared with 5% of the 274 placebo-treated patients in those studies. Adverse reactions that led to treatment discontinuation in a least 2% of drug-treated patients were nausea, insomnia, impotence, headache, dizziness, and somnolence.

Adverse Reactions Occurring at an Incidence of 5% or More

Major Depressive Disorder: Note in particular the following adverse reactions that occurred in at least 5% of the patients receiving venlafaxine hydrochloride extended-release capsules and at a rate at least twice that of the placebo group for all placebo-controlled trials for the major depressive disorder indication (see Table 6): Abnormal ejaculation, gastrointestinal complaints (nausea, dry mouth, and anorexia), CNS complaints (dizziness, somnolence, and abnormal dreams), and sweating. In the two U.S. placebo-controlled trials, the following additional reactions occurred in at least 5% of patients treated with venlafaxine hydrochloride extended-release capsules (n = 192) and at a rate at least twice that of the placebo group: Abnormalities of sexual function (impotence in men, anorgasmia in women, and libido decreased), gastrointestinal complaints (constipation and flatulence), CNS complaints (insomnia, nervousness, and tremor), problems of special senses (abnormal vision), cardiovascular effects (hypertension and vasodilatation), and yawning.

Social Anxiety Disorder: Note in particular the following adverse reactions that occurred in at least 5% of the patients receiving venlafaxine hydrochloride extended-release capsules and at a rate at least twice that of the placebo group for the 2 placebo-controlled trials for the Social Anxiety Disorder indication (see Table 7): Asthenia, gastrointestinal complaints (anorexia, constipation, dry mouth, nausea), CNS complaints (dizziness, insomnia, libido decreased, nervousness, somnolence), abnormalities of sexual function (abnormal ejaculation, impotence, libido decreased, orgasmic dysfunction), yawn, sweating, and abnormal vision.

Adverse Reactions Occurring at an Incidence of 2% or More Among Patients Treated with Venlafaxine Hydrochloride Extended-Release Capsules

Tables 6 and 7 enumerate the incidence, rounded to the nearest percent, of adverse reactions that occurred during acute therapy of major depressive disorder (up to 12 weeks; dose range of 75 to 225 mg/day) and of Social Anxiety Disorder (up to 12 weeks; dose range of 75 to 225 mg/day), respectively, in 2% or more of patients treated with venlafaxine hydrochloride extended-release capsules where the incidence in patients treated with venlafaxine hydrochloride extended-release capsules was greater than the incidence for the respective placebo-treated patients. The table shows the percentage of patients in each group who had at least one episode of a reaction at some time during their treatment. Reported adverse reactions were classified using a standard COSTART-based Dictionary terminology.

The prescriber should be aware that these figures cannot be used to predict the incidence of adverse reactions in the course of usual medical practice where patient characteristics and other factors differ from those which prevailed in the clinical trials. Similarly, the cited frequencies cannot be compared with figures obtained from other clinical investigations involving different treatments, uses and investigators. The cited figures, however, do provide the prescribing physician with some basis for estimating the relative contribution of drug and nondrug factors to the adverse reaction incidence rate in the population studied.

Table 6 Treatment-Emergent Adverse Reaction Incidence in Short-Term Placebo-Controlled Clinical Trials with Venlafaxine Hydrochloride Extended-Release Capsules in Patients with Major Depressive Disorder [Incidence, rounded to the nearest %, for reactions reported by at least 2% of patients treated with venlafaxine hydrochloride extended-release capsules, except for reactions which had an incidence equal to or less than placebo.] , [<1% indicates an incidence greater than zero but less than 1%.]
 | % Reporting Reaction
Body System Preferred Term | Venlafaxine Hydrochloride Extended-Release Capsules | Placebo
 | (n = 357) | (n = 285)
Body as a Whole
Asthenia | 8% | 7%
Cardiovascular System
Vasodilatation [Mostly "hot flashes."] | 4% | 2%
Hypertension | 4% | 1%
Digestive System
Nausea | 31% | 12%
Constipation | 8% | 5%
Anorexia | 8% | 4%
Vomiting | 4% | 2%
Flatulence | 4% | 3%
Metabolic/Nutritional
Weight Loss | 3% | 0%
Nervous System
Dizziness | 20% | 9%
Somnolence | 17% | 8%
Insomnia | 17% | 11%
Dry Mouth | 12% | 6%
Nervousness | 10% | 5%
Abnormal Dreams [Mostly "vivid dreams," "nightmares," and "increased dreaming."] | 7% | 2%
Tremor | 5% | 2%
Depression | 3% | <1%
Paresthesia | 3% | 1%
Libido Decreased | 3% | <1%
Agitation | 3% | 1%
Respiratory System
Pharyngitis | 7% | 6%
Yawn | 3% | 0%
Skin
Sweating | 14% | 3%
Special Senses
Abnormal Vision [Mostly "blurred vision" and "difficulty focusing eyes."] | 4% | <1%
Urogenital System
Abnormal Ejaculation (male) [Mostly "delayed ejaculation."] , [Incidence is based on the number of male patients.] | 16% | <1%
Impotence | 4% | <1%
Anorgasmia (female) [Mostly "delayed orgasm" or "anorgasmia."] , [Incidence is based on the number of female patients.] | 3% | <1%

Table 7 Treatment-Emergent Adverse Reaction Incidence in Short-Term Placebo-Controlled Clinical Trials with Venlafaxine Hydrochloride Extended-Release Capsules in Social Anxiety Disorder Patients [Adverse reactions for which the venlafaxine hydrochloride extended-release capsules reporting rate was less than or equal to the placebo rate are not included.] , [<1% means greater than zero but less than 1%.]
 | % Reporting Reaction
Body System Preferred Term | Venlafaxine Hydrochloride Extended-Release Capsules | Placebo
 | (n =277) | (n = 274)
Body as a Whole
Headache | 34% | 33%
Asthenia | 17% | 8%
Flu Syndrome | 6% | 5%
Accidental Injury | 5% | 3%
Abdominal Pain | 4% | 3%
Cardiovascular System
Hypertension | 5% | 4%
Vasodilatation [Mostly "hot flashes."] | 3% | 1%
Palpitation | 3% | 1%
Digestive System
Nausea | 29% | 9%
Anorexia [Mostly "decreased appetite" and "loss of appetite."] | 20% | 1%
Constipation | 8% | 4%
Diarrhea | 6% | 5%
Vomiting | 3% | 2%
Eructation | 2% | 0%
Metabolic/Nutritional
Weight Loss | 4% | 0%
Nervous System
Insomnia | 23% | 7%
Dry Mouth | 17% | 4%
Dizziness | 16% | 8%
Somnolence | 16% | 8%
Nervousness | 11% | 3%
Libido Decreased | 9% | <1%
Anxiety | 5% | 3%
Agitation | 4% | 1%
Tremor | 4% | <1%
Abnormal Dreams [Mostly "vivid dreams," "nightmares," and "increased dreaming."] | 4% | <1%
Paresthesia | 3% | <1%
Twitching | 2% | 0%
Respiratory System
Yawn | 5% | <1%
Sinusitis | 2% | 1%
Skin
Sweating | 13% | 2%
Special Senses
Abnormal Vision [Mostly "blurred vision."] | 6% | 3%
Urogenital System
Abnormal Ejaculation [Includes "delayed ejaculation" and "anorgasmia."] , [Percentage based on the number of males (venlafaxine hydrochloride extended-release capsules = 158, placebo = 153).] | 16% | 1%
Impotence | 10% | 1%
Orgasmic Dysfunction [Includes "abnormal orgasm" and "anorgasmia."] , [Percentage based on the number of females (venlafaxine hydrochloride extended-release capsules = 119, placebo = 121).] | 8% | 0%

Vital Sign Changes

Treatment with venlafaxine hydrochloride extended-release capsules treatment for up to 12 weeks in premarketing placebo-controlled major depressive disorder trials was associated with a mean final on-therapy increase in pulse rate of approximately 2 beats per minute, compared with 1 beat per minute for placebo.

Treatment with venlafaxine hydrochloride extended-release capsules for up to 12 weeks in premarketing placebo-controlled Social Anxiety Disorder trials was associated with a mean final on-therapy increase in pulse rate of approximately 4 beats per minute, compared with an increase of 1 beat per minute for placebo. [See Warnings and Precautions (5.4) for effects on blood pressure.]

In a flexible-dose study in MDD, with doses of venlafaxine hydrochloride immediate-release tablets in the range of 200 to 375 mg/day and mean dose greater than 300 mg/day, the mean pulse was increased by about 2 beats per minute compared with a decrease of about 1 beat per minute for placebo. [See Warnings and Precautions (5.17) for effects on heart rate.]

Laboratory Changes

Serum Cholesterol

Venlafaxine hydrochloride extended-release capsules treatment for up to 12 weeks in premarketing placebo-controlled trials for major depressive disorder was associated with a mean final on-therapy increase in serum cholesterol concentration of approximately 1.5 mg/dL compared with a mean final decrease of 7.4 mg/dL for placebo. Venlafaxine hydrochloride extended-release capsules treatment for up to 12 weeks in other premarketing placebo-controlled trials was associated with mean final on-therapy increases in serum cholesterol concentration of approximately 7.9 mg/dL compared with a mean final decrease of 2.9 mg/dL for placebo.

Patients treated with venlafaxine hydrochloride immediate-release tablets for at least 3 months in placebo-controlled 12-month extension trials had a mean final on-therapy increase in total cholesterol of 9.1 mg/dL compared with a decrease of 7.1 mg/dL among placebo-treated patients. This increase was duration dependent over the study period and tended to be greater with higher doses. Clinically relevant increases in serum cholesterol, defined as 1) a final on-therapy increase in serum cholesterol ≥50 mg/dL from baseline and to a value ≥261 mg/dL, or 2) an average on-therapy increase in serum cholesterol ≥50 mg/dL from baseline and to a value ≥261 mg/dL, were recorded in 5.3% of venlafaxine-treated patients and 0.0% of placebo-treated patients [see Warnings and Precautions (5.15)].

Serum Triglycerides

Venlafaxine hydrochloride extended-release capsules treatment for up to 12 weeks in pooled premarketing trials was associated with a mean final on-therapy increase in fasting serum triglyceride concentration of approximately 8.2 mg/dl, compared with a mean final increase of 0.4 mg/dl for placebo.

ECG Changes

In a flexible-dose MDD study with doses of venlafaxine hydrochloride immediate-release tablets in the range of 200 to 375 mg/day and mean dose greater than 300 mg/day, the mean change in heart rate was 8.5 beats per minute compared with 1.7 beats per minute for placebo. [See Warnings and Precautions (5.17)]

Other Adverse Reactions Observed During the Premarketing Evaluation of Venlafaxine Hydrochloride Immediate-Release Tablets and Venlafaxine Hydrochloride Extended-Release Capsules

During its premarketing assessment, multiple doses of venlafaxine hydrochloride extended-release capsules were administered to 705 patients in Phase 3 major depressive disorder studies and venlafaxine hydrochloride immediate-release tablets was administered to 96 patients. During its premarketing assessment, multiple doses of venlafaxine hydrochloride extended-release capsules were also administered to 3514 patients in other Phase 3 studies. In addition, in premarketing assessment of venlafaxine hydrochloride immediate-release tablets, multiple doses were administered to 2897 patients in Phase 2 to Phase 3 studies for major depressive disorder. The conditions and duration of exposure to venlafaxine in both development programs varied greatly, and included (in overlapping categories) open and double-blind studies, uncontrolled and controlled studies, inpatient (venlafaxine hydrochloride immediate-release tablets only) and outpatient studies, fixed-dose, and titration studies. Adverse reactions associated with this exposure were recorded by clinical investigators using terminology of their own choosing. Consequently, it is not possible to provide a meaningful estimate of the proportion of individuals experiencing adverse reactions without first grouping similar types of untoward events into a smaller number of standardized reaction categories.

In the tabulations that follow, reported adverse reactions were classified using a standard COSTART-based Dictionary terminology. The frequencies presented, therefore, represent the proportion of the 7212 patients exposed to multiple doses of either formulation of venlafaxine who experienced a reaction of the type cited on at least one occasion while receiving venlafaxine. All reported reactions are included except those already listed in Tables 6 and 7 and those reactions for which a drug cause was remote. If the COSTART term for a reaction was so general as to be uninformative, it was replaced with a more informative term. It is important to emphasize that, although the reactions reported occurred during treatment with venlafaxine, they were not necessarily caused by it.

Reactions are further categorized by body system and listed in order of decreasing frequency using the following definitions: frequent adverse reactions are defined as those occurring on one or more occasions in at least 1/100 patients; infrequent adverse reactions are those occurring in 1/100 to 1/1000 patients; rare reactions are those occurring in fewer than 1/1000 patients.

Body as a whole - Frequent: chest pain substernal, chills, fever, neck pain; Infrequent: face edema, intentional injury, malaise, moniliasis, neck rigidity, pelvic pain, photosensitivity reaction, suicide attempt, withdrawal syndrome; Rare: appendicitis, bacteremia, cellulitis, granuloma.

Cardiovascular system - Frequent: migraine, tachycardia; Infrequent: angina pectoris, bradycardia, extrasystoles, hypotension, peripheral vascular disorder (mainly cold feet and/or cold hands), postural hypotension, syncope; Rare: aortic aneurysm, arteritis, first-degree atrioventricular block, bigeminy, bundle branch block, capillary fragility, cerebral ischemia, coronary artery disease, congestive heart failure, heart arrest, hematoma, cardiovascular disorder (mitral valve and circulatory disturbance), mucocutaneous hemorrhage, myocardial infarct, pallor, sinus arrhythmia, thrombophlebitis.

Digestive system - Frequent: increased appetite; Infrequent: bruxism, colitis, dysphagia, tongue edema, eructation, esophagitis, gastritis, gastroenteritis, gastrointestinal ulcer, gingivitis, glossitis, rectal hemorrhage, hemorrhoids, melena, oral moniliasis, stomatitis, mouth ulceration; Rare: abdominal distension, biliary pain, cheilitis, cholecystitis, cholelithiasis, esophageal spasms, duodenitis, hematemesis, gastroesophageal reflux disease, gastrointestinal hemorrhage, gum hemorrhage, hepatitis, ileitis, jaundice, intestinal obstruction, liver tenderness, parotitis, periodontitis, proctitis, salivary gland enlargement, increased salivation, soft stools, tongue discoloration.

Endocrine system - Rare: galactorrhoea, goiter, hyperthyroidism, hypothyroidism, thyroid nodule, thyroiditis.

Hemic and lymphatic system - Frequent: ecchymosis; Infrequent: anemia, leukocytosis, leukopenia, lymphadenopathy, thrombocythemia; Rare: basophilia, bleeding time increased, cyanosis, eosinophilia, lymphocytosis, multiple myeloma, purpura, thrombocytopenia.

Metabolic and nutritional - Frequent: edema, weight gain; Infrequent: alkaline phosphatase increased, dehydration, hypercholesteremia, hyperglycemia, hyperlipidemia, hypokalemia, SGOT (AST) increased, SGPT (ALT) increased, thirst; Rare: alcohol intolerance, bilirubinemia, BUN increased, creatinine increased, diabetes mellitus, glycosuria, gout, healing abnormal, hemochromatosis, hypercalcinuria, hyperkalemia, hyperphosphatemia, hyperuricemia, hypocholesteremia, hypoglycemia, hyponatremia, hypophosphatemia, hypoproteinemia, uremia.

Musculoskeletal system - Infrequent: arthritis, arthrosis, bone spurs, bursitis, leg cramps, myasthenia, tenosynovitis; Rare: pathological fracture, muscle cramp, muscle spasms, musculoskeletal stiffness, myopathy, osteoporosis, osteosclerosis, plantar fasciitis, rheumatoid arthritis, tendon rupture.

Nervous system - Frequent: amnesia, confusion, depersonalization, hypesthesia, trismus, vertigo; Infrequent: akathisia, apathy, ataxia, circumoral paresthesia, CNS stimulation, emotional lability, euphoria, hallucinations, hostility, hyperesthesia, hyperkinesia, hypotonia, incoordination, libido increased, manic reaction, myoclonus, neuralgia, neuropathy, psychosis, seizure, stupor, suicidal ideation; Rare: akinesia, alcohol abuse, aphasia, bradykinesia, buccoglossal syndrome, cerebrovascular accident, feeling drunk, loss of consciousness, delusions, dementia, dystonia, energy increased, facial paralysis, abnormal gait, Guillain-Barre Syndrome, homicidal ideation, hyperchlorhydria, hypokinesia, hysteria, impulse control difficulties, motion sickness, neuritis, nystagmus, paranoid reaction, paresis, psychotic depression, reflexes decreased, reflexes increased, torticollis.

Respiratory system - Frequent: cough increased, dyspnea; Infrequent: asthma, chest congestion, epistaxis, hyperventilation, laryngismus, laryngitis, pneumonia; Rare: atelectasis, hemoptysis, hypoventilation, hypoxia, larynx edema, pleurisy, pulmonary embolus, sleep apnea.

Skin and appendages - Frequent: pruritus; Infrequent: acne, alopecia, contact dermatitis, dry skin, eczema, maculopapular rash, psoriasis, urticaria; Rare: brittle nails, erythema nodosum, exfoliative dermatitis, lichenoid dermatitis, furunculosis, hirsutism, leukoderma, miliaria, petechial rash, pruritic rash, pustular rash, vesiculobullous rash, seborrhea, skin atrophy, skin hypertrophy, skin striae, sweating decreased.

Special senses - Frequent: abnormality of accommodation, mydriasis, taste perversion; Infrequent: conjunctivitis, diplopia, dry eyes, otitis media, parosmia, photophobia, taste loss; Rare: blepharitis, cataract, chromatopsia, conjunctival edema, corneal lesion, deafness, exophthalmos, eye hemorrhage, glaucoma, retinal hemorrhage, subconjunctival hemorrhage, hyperacusis, keratitis, labyrinthitis, miosis, papilledema, decreased pupillary reflex, otitis externa, scleritis, uveitis, visual field defect.

Urogenital system - Frequent: albuminuria, urination impaired; Infrequent: amenorrhea, [Based on the number of men and women as appropriate.] cystitis, dysuria, hematuria, kidney calculus, kidney pain, leukorrhea, menorrhagia, metrorrhagia, nocturia, breast pain, polyuria, pyuria, prostatic disorder (prostatitis, enlarged prostate, and prostate irritability), urinary incontinence, urinary retention, urinary urgency, vaginal hemorrhage, vaginitis; Rare: abortion, anuria, breast discharge, breast engorgement, balanitis, breast enlargement, endometriosis, female lactation, fibrocystic breast, calcium crystalluria, cervicitis, orchitis, ovarian cyst, bladder pain, prolonged erection, gynecomastia (male), hypomenorrhea, mastitis, menopause, pyelonephritis, oliguria, salpingitis, urolithiasis, uterine hemorrhage, uterine spasm, vaginal dryness.

6.2 Post-Marketing Experience

Voluntary reports of other adverse reactions temporally associated with the use of venlafaxine have been received since market introduction. Because these reactions are reported from a population of uncertain size, it is not always possible to reliably estimate their frequency or establish a causal relationship to drug exposure. These reports include the following reactions: agranulocytosis, anaphylaxis, aplastic anemia, catatonia, congenital anomalies, impaired coordination and balance, CPK increased, deep vein thrombophlebitis, delirium, EKG abnormalities such as QT prolongation; cardiac arrhythmias including atrial fibrillation, supraventricular tachycardia, ventricular extrasystoles, and rare reports of ventricular fibrillation and ventricular tachycardia, including torsade de pointes; toxic epidermal necrolysis/Stevens-Johnson Syndrome, erythema multiforme, extrapyramidal symptoms (including dyskinesia and tardive dyskinesia), angle-closure glaucoma, hemorrhage (including eye and gastrointestinal bleeding), hepatic reactions (including GGT elevation; abnormalities of unspecified liver function tests; liver damage, necrosis, or failure; and fatty liver), interstitial lung disease, involuntary movements, LDH increased, neutropenia, night sweats, pancreatitis, pancytopenia, panic, prolactin increased, renal failure, rhabdomyolysis, shock-like electrical sensations or tinnitus (in some cases, subsequent to the discontinuation of venlafaxine or tapering of dose), and syndrome of inappropriate antidiuretic hormone secretion (usually in the elderly).

7 DRUG INTERACTIONS

7.1 Alcohol

A single dose of ethanol (0.5 g/kg) had no effect on the pharmacokinetics of venlafaxine or O-desmethylvenlafaxine (ODV) when venlafaxine was administered at 150 mg/day in 15 healthy male subjects. Additionally, administration of venlafaxine in a stable regimen did not exaggerate the psychomotor and psychometric effects induced by ethanol in these same subjects when they were not receiving venlafaxine.

7.2 Cimetidine

Concomitant administration of cimetidine and venlafaxine in a steady-state study for both drugs resulted in inhibition of first-pass metabolism of venlafaxine in 18 healthy subjects. The oral clearance of venlafaxine was reduced by about 43%, and the exposure (AUC) and maximum concentration (Cmax) of the drug were increased by about 60%. However, coadministration of cimetidine had no apparent effect on the pharmacokinetics of ODV, which is present in much greater quantity in the circulation than venlafaxine. The overall pharmacological activity of venlafaxine plus ODV is expected to increase only slightly, and no dosage adjustment should be necessary for most normal adults. However, for patients with pre-existing hypertension, and for elderly patients or patients with hepatic dysfunction, the interaction associated with the concomitant use of venlafaxine and cimetidine is not known and potentially could be more pronounced. Therefore, caution is advised with such patients.

7.3 Diazepam

Under steady-state conditions for venlafaxine administered at 150 mg/day, a single 10 mg dose of diazepam did not appear to affect the pharmacokinetics of either venlafaxine or ODV in 18 healthy male subjects. Venlafaxine also did not have any effect on the pharmacokinetics of diazepam or its active metabolite, desmethyldiazepam, or affect the psychomotor and psychometric effects induced by diazepam.

7.4 Haloperidol

Venlafaxine administered under steady-state conditions at 150 mg/day in 24 healthy subjects decreased total oral-dose clearance (Cl/F) of a single 2 mg dose of haloperidol by 42%, which resulted in a 70% increase in haloperidol AUC. In addition, the haloperidol Cmax increased 88% when coadministered with venlafaxine, but the haloperidol elimination half-life (t1/2) was unchanged. The mechanism explaining this finding is unknown.

7.5 Lithium

The steady-state pharmacokinetics of venlafaxine administered at 150 mg/day were not affected when a single 600 mg oral dose of lithium was administered to 12 healthy male subjects. ODV also was unaffected. Venlafaxine had no effect on the pharmacokinetics of lithium (see also CNS-Active Drugs, below).

7.6 Drugs Highly Bound to Plasma Proteins

Venlafaxine is not highly bound to plasma proteins; therefore, administration of Venlafaxine Extended Release Tablets to a patient taking another drug that is highly protein bound should not cause increased free concentrations of the other drug.

7.7 Drugs that Inhibit Cytochrome P450 Isoenzymes

CYP2D6 Inhibitors: In vitro and in vivo studies indicate that venlafaxine is metabolized to its active metabolite, ODV, by CYP2D6, the isoenzyme that is responsible for the genetic polymorphism seen in the metabolism of many antidepressants. Therefore, the potential exists for a drug interaction between drugs that inhibit CYP2D6-mediated metabolism of venlafaxine, reducing the metabolism of venlafaxine to ODV, resulting in increased plasma concentrations of venlafaxine and decreased concentrations of the active metabolite. CYP2D6 inhibitors such as quinidine would be expected to do this, but the effect would be similar to what is seen in patients who are genetically CYP2D6 poor metabolizers [see Clinical Pharmacology (12.3)]. Therefore, no dosage adjustment is required when venlafaxine is coadministered with a CYP2D6 inhibitor.

Ketoconazole: A pharmacokinetic study with ketoconazole 100 mg b.i.d. with a single dose of venlafaxine 50 mg in extensive metabolizers (EM; n=14) and 25 mg in poor metabolizers (PM; n=6) of CYP2D6 resulted in higher plasma concentrations of both venlafaxine and O-desmethylvenlafaxine (ODV) in most subjects following administration of ketoconazole. Venlafaxine Cmax increased by 26% in EM subjects and 48% in PM subjects. Cmax values for ODV increased by 14% and 29% in EM and PM subjects, respectively.

Venlafaxine AUC increased by 21% in EM subjects and 70% in PM subjects (range in PM's -2% to 206%), and AUC values for ODV increased by 23% and 33% in EM and PM (range in PM's -38% to 105%) subjects, respectively.

Combined AUC's of venlafaxine and ODV increased on average by approximately 23% in EM's and 53% in PM's, (range in PM's 4% - 134%).

Concomitant use of CYP3A4 inhibitors and venlafaxine may increase levels of venlafaxine and ODV. Therefore, caution is advised if a patient's therapy includes a CYP3A4 inhibitor and venlafaxine concomitantly.

7.8 Drugs Metabolized by Cytochrome P450 Isoenzymes

CYP2D6

In vitro studies indicate that venlafaxine is a relatively weak inhibitor of CYP2D6. These findings have been confirmed in a clinical drug interaction study comparing the effect of venlafaxine with that of fluoxetine on the CYP2D6-mediated metabolism of dextromethorphan to dextrorphan.

Imipramine - Venlafaxine did not affect the pharmacokinetics of imipramine and 2-OH-imipramine. However, desipramine AUC, Cmax, and Cmin increased by about 35% in the presence of venlafaxine. The 2-OH-desipramine AUC's increased by at least 2.5 fold (with venlafaxine 37.5 mg q12h) and by 4.5 fold (with venlafaxine 75 mg q12h). Imipramine did not affect the pharmacokinetics of venlafaxine and ODV. The clinical significance of elevated 2-OH-desipramine levels is unknown.

Metoprolol - Concomitant administration of venlafaxine (50 mg every 8 hours for 5 days) and metoprolol (100 mg every 24 hours for 5 days) to 18 healthy male subjects in a pharmacokinetic interaction study for both drugs resulted in an increase of plasma concentrations of metoprolol by approximately 30-40% without altering the plasma concentrations of its active metabolite, α-hydroxymetoprolol. Metoprolol did not alter the pharmacokinetic profile of venlafaxine or its active metabolite, O-desmethylvenlafaxine.

Venlafaxine appeared to reduce the blood pressure lowering effect of metoprolol in this study. The clinical relevance of this finding for hypertensive patients is unknown. Caution should be exercised with co-administration of venlafaxine and metoprolol.

Venlafaxine treatment has been associated with dose-related increases in blood pressure in some patients. It is recommended that patients receiving Venlafaxine Extended Release Tablets have regular monitoring of blood pressure [see Warnings and Precautions (5.5)].

Risperidone - Venlafaxine administered under steady-state conditions at 150 mg/day slightly inhibited the CYP2D6-mediated metabolism of risperidone (administered as a single 1 mg oral dose) to its active metabolite, 9-hydroxyrisperidone, resulting in an approximate 32% increase in risperidone AUC. However, venlafaxine coadministration did not significantly alter the pharmacokinetic profile of the total active moiety (risperidone plus 9-hydroxyrisperidone).

CYP3A4

Venlafaxine did not inhibit CYP3A4 in vitro. This finding was confirmed in vivo by clinical drug interaction studies in which venlafaxine did not inhibit the metabolism of several CYP3A4 substrates, including alprazolam, diazepam, and terfenadine.

Indinavir - In a study of 9 healthy volunteers, venlafaxine administered under steady-state conditions at 150 mg/day resulted in a 28% decrease in the AUC of a single 800 mg oral dose of indinavir and a 36% decrease in indinavir Cmax. Indinavir did not affect the pharmacokinetics of venlafaxine and ODV. The clinical significance of this finding is unknown.

CYP1A2

Venlafaxine did not inhibit CYP1A2 in vitro. This finding was confirmed in vivo by a clinical drug interaction study in which venlafaxine did not inhibit the metabolism of caffeine, a CYP1A2 substrate.

CYP2C9

Venlafaxine did not inhibit CYP2C9 in vitro. In vivo, venlafaxine 75 mg by mouth every 12 hours did not alter the pharmacokinetics of a single 500 mg dose of tolbutamide or the CYP2C9 mediated formation of 4-hydroxy-tolbutamide.

CYP2C19

Venlafaxine did not inhibit the metabolism of diazepam, which is partially metabolized by CYP2C19 (see Diazepam above).

7.9 Monoamine Oxidase Inhibitors

See Contraindications (4) and Warnings and Precautions (5.2).

7.10 Other CNS-Active Drugs

The risk of using venlafaxine in combination with other CNS-active drugs has not been systematically evaluated (except in the case of those CNS-active drugs noted above). Consequently, caution is advised if the concomitant administration of venlafaxine and such drugs is required.

Serotonergic Drugs

Based on the mechanism of action of Venlafaxine Extended Release Tablets and the potential for serotonin syndrome, caution is advised when Venlafaxine Extended Release Tablets are co-administered with other drugs that may affect the serotonergic neurotransmitter systems, such as triptans, SSRIs, other SNRIs, linezolid (an antibiotic which is a reversible non-selective MAOI), lithium, tramadol, or St. John's Wort [see Warnings and Precautions (5.3)]. If concomitant treatment of Venlafaxine Extended Release Tablets with these drugs is clinically warranted, careful observation of the patient is advised, particularly during treatment initiation and dose increases [see Warnings and Precautions (5.3)]. The concomitant use of Venlafaxine Extended Release Tablets with tryptophan supplements is not recommended [see Warnings and Precautions (5.3)].

Triptans

There have been rare postmarketing reports of serotonin syndrome with use of an SSRI and a triptan. If concomitant treatment of Venlafaxine Extended Release Tablets with a triptan is clinically warranted, careful observation of the patient is advised, particularly during treatment initiation and dose increases [see Warnings and Precautions (5.3)].

7.11 Drugs that Interfere with Hemostasis (e.g., NSAID's, Aspirin, and Warfarin)

Serotonin release by platelets plays an important role in hemostasis. Epidemiological studies of the case-control and cohort design that have demonstrated an association between use of psychotropic drugs that interfere with serotonin reuptake and the occurrence of upper gastrointestinal bleeding. These studies have also shown that concurrent use of an NSAID or aspirin may potentiate this risk of bleeding. Altered anticoagulant effects, including increased bleeding, have been reported when SSRI's and SNRI's are coadministered with warfarin. Patients receiving warfarin therapy should be carefully monitored when Venlafaxine Extended-Release Tablets are initiated or discontinued. [See Warnings and Precautions (5.14).]

7.12 Electroconvulsive Therapy

There are no clinical data establishing the benefit of electroconvulsive therapy combined with Venlafaxine Extended Release Tablets treatment.

7.13 Postmarketing Spontaneous Drug Interaction Reports

There have been reports of elevated clozapine levels that were temporally associated with adverse reactions, including seizures, following the addition of venlafaxine.

There have been reports of increases in prothrombin time, partial thromboplastin time, or INR when venlafaxine was given to patients receiving warfarin therapy.

8 USE IN SPECIFIC POPULATIONS

8.1 Pregnancy

Teratogenic Effects

Pregnancy Category C

Venlafaxine did not cause malformations in offspring of rats or rabbits given doses up to 2.5 times (rat) or 4 times (rabbit) the maximum recommended human daily dose on a mg/m^2 basis. However, in rats, there was a decrease in pup weight, an increase in stillborn pups, and an increase in pup deaths during the first 5 days of lactation, when dosing began during pregnancy and continued until weaning. The cause of these deaths is not known. These effects occurred at 2.5 times (mg/m^2) the maximum human daily dose. The no effect dose for rat pup mortality was 0.25 times the human dose on a mg/m^2 basis. There are no adequate and well-controlled studies in pregnant women. Because animal reproduction studies are not always predictive of human response, this drug should be used during pregnancy only if clearly needed.

Non-Teratogenic Effects

Neonates exposed to venlafaxine hydrochloride extended-release capsules, other SNRIs (Serotonin and Norepinephrine Reuptake Inhibitors), or SSRIs (Selective Serotonin Reuptake Inhibitors), late in the third trimester have developed complications requiring prolonged hospitalization, respiratory support, and tube feeding. Such complications can arise immediately upon delivery. Reported clinical findings have included respiratory distress, cyanosis, apnea, seizures, temperature instability, feeding difficulty, vomiting, hypoglycemia, hypotonia, hypertonia, hyperreflexia, tremor, jitteriness, irritability, and constant crying. These features are consistent with either a direct toxic effect of SSRIs and SNRIs or, possibly, a drug discontinuation syndrome. It should be noted that, in some cases, the clinical picture is consistent with serotonin syndrome [see Warnings and Precautions (5.3)]. When treating a pregnant woman with Venlafaxine Extended-Release Tablets during the third trimester, the physician should carefully consider the potential risks and benefits of treatment [see Dosage and Administration (2)].

8.2 Labor and Delivery

The effect of venlafaxine on labor and delivery in humans is unknown.

8.3 Nursing Mothers

Venlafaxine and ODV have been reported to be excreted in human milk. Because of the potential for serious adverse reactions in nursing infants from Venlafaxine Extended Release Tablets, a decision should be made whether to discontinue nursing or to discontinue the drug, taking into account the importance of the drug to the mother.

8.4 Pediatric Use

Safety and effectiveness in the pediatric population have not been established [see BOXED WARNING and Warnings and Precautions (5.1)]. Two placebo-controlled trials in 766 pediatric patients with MDD and two placebo-controlled trials in another disorder in 793 pediatric patients have been conducted with venlafaxine hydrochloride extended-release capsules, and the data were not sufficient to support a claim for use in pediatric patients.

Anyone considering the use of Venlafaxine Extended Release Tablets in a child or adolescent must balance the potential risks with the clinical need.

Although no studies have been designed to primarily assess impact of venlafaxine hydrochloride extended-release capsules on the growth, development, and maturation of children and adolescents, the studies that have been done suggest that Venlafaxine Extended Release Tablets may adversely affect weight and height [see Warnings and Precautions (5.8, 5.9, and 5.10)]. Should the decision be made to treat a pediatric patient with Venlafaxine Extended Release Tablets, regular monitoring of weight and height is recommended during treatment, particularly if it is to be continued long term. The safety of Venlafaxine Extended Release Tablets treatment for pediatric patients has not been systematically assessed for chronic treatment longer than six months in duration.

In the studies conducted in pediatric patients (ages 6-17), the occurrence of blood pressure and cholesterol increases considered to be clinically relevant in pediatric patients was similar to that observed in adult patients. Consequently, the precautions for adults apply to pediatric patients [see Warnings and Precautions (5.4 and 5.15)].

8.5 Geriatric Use

Approximately 4% (14/357) and 2% (6/277) of patients treated with venlafaxine hydrochloride extended-release capsules in placebo-controlled premarketing major depressive disorder and Social Anxiety Disorder trials, respectively, were 65 years of age or over. Of 2,897 patients treated with venlafaxine hydrochloride immediate-release tablets in premarketing phase major depressive disorder studies, 12% (357) were 65 years of age or over. No overall differences in effectiveness or safety were observed between geriatric patients and younger patients, and other reported clinical experience generally has not identified differences in response between the elderly and younger patients. However, greater sensitivity of some older individuals cannot be ruled out. SSRIs and SNRIs, including venlafaxine hydrochloride extended-release capsules have been associated with cases of clinically significant hyponatremia in elderly patients, who may be at greater risk for this adverse reaction [see Warnings and Precautions (5.12)].

The pharmacokinetics of venlafaxine and ODV are not substantially altered in the elderly [see Clinical Pharmacology (12.3)]. No dose adjustment is recommended for the elderly on the basis of age alone, although other clinical circumstances, some of which may be more common in the elderly, such as renal or hepatic impairment, may warrant a dose reduction [see Dosage and Administration (2.3)].

8.6 Patients with Hepatic Impairment

In patients with cirrhosis of the liver, the clearances of venlafaxine and its active metabolite (ODV) were decreased, thus prolonging the elimination half-lives of these substances. A large degree of intersubject variability was noted. [See Clinical Pharmacology (12.3).] A lower dose and individualization of dosing may be necessary [see Dosage and Administration (2.3)]. Venlafaxine Extended-Release Tablets, like all drugs effective in the treatment of major depressive disorder, should be used with caution in such patients.

8.7 Patients with Renal Impairment

In patients with renal impairment (GFR = 10 to 70 mL/min), the clearances of venlafaxine and its active metabolites were decreased, thus prolonging the elimination half-lives of these substances [see Clinical Pharmacology (12.3)]. It is recommended that the total daily dose be reduced by 25% to 50% in patients with renal impairment. Because there was much individual variability in clearance between patients with renal impairment, individualization of dosage may be desirable in some patients. In patients undergoing hemodialysis, it is recommended that the total daily dose be reduced by 50%. [See Dosage and Administration (2.3).] Venlafaxine Extended Release Tablets, like all drugs effective in the treatment of major depressive disorder, should be used with caution in such patients.

9 DRUG ABUSE AND DEPENDENCE

9.1 Controlled Substance

Venlafaxine Extended Release Tablets (venlafaxine hydrochloride) are not a controlled substance.

9.2 Abuse

While venlafaxine has not been systematically studied in clinical trials for its potential for abuse, there was no indication of drug-seeking behavior in the clinical trials. However, it is not possible to predict on the basis of premarketing experience the extent to which a CNS active drug will be misused, diverted, and/or abused once marketed. Consequently, physicians should carefully evaluate patients for history of drug abuse and follow such patients closely, observing them for signs of misuse or abuse of venlafaxine (e.g., development of tolerance, incrementations of dose, drug-seeking behavior).

9.3 Dependence

In vitro studies revealed that venlafaxine has virtually no affinity for opiate, benzodiazepine, phencyclidine (PCP), or N-methyl-D-aspartic acid (NMDA) receptors.

Venlafaxine was not found to have any significant CNS stimulant activity in rodents. In primate drug discrimination studies, venlafaxine showed no significant stimulant or depressant abuse liability.

Discontinuation effects have been reported in patients receiving venlafaxine [see Dosage and Administration (2.4) and Warnings and Precautions (5.6)].

10 OVERDOSAGE

10.1 Human Experience

Among the patients included in the premarketing evaluation of venlafaxine hydrochloride extended-release capsules, there were 2 reports of acute overdosage with venlafaxine hydrochloride extended-release capsules in major depressive disorder trials, either alone or in combination with other drugs. One patient took a combination of 6 g of venlafaxine hydrochloride extended-release capsules and 2.5 mg of lorazepam. This patient was hospitalized, treated symptomatically, and recovered without any untoward effects. The other patient took 2.85 g of venlafaxine hydrochloride extended-release capsules. This patient reported paresthesia of all four limbs but recovered without sequelae.

There were no reports of acute overdose with venlafaxine hydrochloride extended-release capsules in Social Anxiety Disorder trials.

Among the patients included in the premarketing evaluation with venlafaxine hydrochloride immediate-release tablets, there were 14 reports of acute overdose with venlafaxine, either alone or in combination with other drugs and/or alcohol. The majority of the reports involved ingestion in which the total dose of venlafaxine taken was estimated to be no more than several-fold higher than the usual therapeutic dose. The 3 patients who took the highest doses were estimated to have ingested approximately 6.75 g, 2.75 g, and 2.5 g. The resultant peak plasma levels of venlafaxine for the latter 2 patients were 6.24 and 2.35 µg/mL, respectively, and the peak plasma levels of O-desmethylvenlafaxine were 3.37 and 1.30 µg/mL, respectively. Plasma venlafaxine levels were not obtained for the patient who ingested 6.75 g of venlafaxine. All 14 patients recovered without sequelae. Most patients reported no symptoms. Among the remaining patients, somnolence was the most commonly reported symptom. The patient who ingested 2.75 g of venlafaxine was observed to have 2 generalized convulsions and a prolongation of QTc to 500 msec, compared with 405 msec at baseline. Mild sinus tachycardia was reported in 2 of the other patients.

In postmarketing experience, overdose with venlafaxine has occurred predominantly in combination with alcohol and/or other drugs. The most commonly reported reactions in overdosage include tachycardia, changes in level of consciousness (ranging from somnolence to coma), mydriasis, seizures, and vomiting. Electrocardiogram changes (e.g., prolongation of QT interval, bundle branch block, QRS prolongation), ventricular tachycardia, bradycardia, hypotension, rhabdomyolysis, vertigo, liver necrosis, serotonin syndrome, and death have been reported.

Published retrospective studies report that venlafaxine overdosage may be associated with an increased risk of fatal outcomes compared to that observed with SSRI antidepressant products, but lower than that for tricyclic antidepressants. Epidemiological studies have shown that venlafaxine-treated patients have a higher pre-existing burden of suicide risk factors than SSRI-treated patients. The extent to which the finding of an increased risk of fatal outcomes can be attributed to the toxicity of venlafaxine in overdosage as opposed to some characteristic(s) of venlafaxine-treated patients is not clear. Prescriptions for Venlafaxine Extended Release Tablets should be written for the smallest quantity of tablets consistent with good patient management, in order to reduce the risk of overdose.

10.2 Management of Overdosage

Treatment should consist of those general measures employed in the management of overdosage with any antidepressant.

Ensure an adequate airway, oxygenation, and ventilation. Monitor cardiac rhythm and vital signs. General supportive and symptomatic measures are also recommended. Induction of emesis is not recommended. Gastric lavage with a large bore orogastric tube with appropriate airway protection, if needed, may be indicated if performed soon after ingestion or in symptomatic patients.

Activated charcoal should be administered. Due to the large volume of distribution of this drug, forced diuresis, dialysis, hemoperfusion, and exchange transfusion are unlikely to be of benefit. No specific antidotes for venlafaxine are known.

In managing overdosage, consider the possibility of multiple drug involvement. The physician should consider contacting a poison control center for additional information on the treatment of any overdose. Telephone numbers for certified poison control centers are listed in the Physicians' Desk Reference® (PDR).

11 DESCRIPTION

Venlafaxine Extended Release Tablets (venlafaxine hydrochloride) are extended-release tablets for oral administration that contain venlafaxine hydrochloride, a structurally novel antidepressant. Venlafaxine hydrochloride is a selective serotonin and norepinephrine reuptake inhibitor (SNRI). It is designated (R/S)-1-[2-(dimethylamino)-1-(4-methoxyphenyl)ethyl] cyclohexanol hydrochloride or (±)-1-[α- [(dimethylamino)methyl]-p-methoxybenzyl] cyclohexanol hydrochloride and has the empirical formula of C17H27NO2 HCl. Its molecular weight is 313.87. The structural formula is shown below.

Venlafaxine hydrochloride

Venlafaxine hydrochloride

Venlafaxine hydrochloride is a white to off-white crystalline solid with a solubility of 572 mg/mL in water (adjusted to ionic strength of 0.2 M with sodium chloride). Its octanol:water (0.2 M sodium chloride) partition coefficient is 0.43. Venlafaxine Extended Release Tablets are formulated as extended-release tablet for once-a-day oral administration. Venlafaxine Extended Release Tablets use osmotic pressure to deliver venlafaxine hydrochloride at a controlled rate over approximately 24 hours. The system, which resembles a conventional tablet in appearance, comprises an osmotically active core surrounded by a semipermeable membrane. The unitary tablet core is composed of the drug and excipients (including the osmotically active components). There is a precision-laser drilled orifice in the semipermeable membrane on the side of the tablet. In an aqueous environment, such as the gastrointestinal tract, water permeates through the membrane into the tablet core, causing the drug to dissolve and the osmotic components to expand. This expansion pushes the drug out through the orifice. The semipermeable membrane controls the rate at which water permeates into the tablet core, which in turn controls the rate of drug delivery. The controlled rate of drug delivery into the gastrointestinal lumen is thus independent of pH or gastrointestinal motility. The function of Venlafaxine Extended Release Tablets depends on the existence of an osmotic gradient between the contents of the core and the fluid in the gastrointestinal tract. Since the osmotic gradient remains constant, drug delivery remains essentially constant.

The biologically inert components of the tablet remain intact during gastrointestinal transit and are eliminated in the feces as an insoluble shell.

Tablets contain venlafaxine hydrochloride equivalent to 37.5 mg, 75 mg, 150 mg, or 225 mg venlafaxine. Inactive ingredients consist of mannitol, povidone, microcrystalline cellulose, polyethylene glycol, colloidal silicon dioxide, magnesium stearate, cellulose acetate, hypromellose, lactose, titanium dioxide, triacetin, black iron oxide, and propylene glycol.

12 CLINICAL PHARMACOLOGY

12.1 Mechanism of Action

The mechanism of the antidepressant action of venlafaxine in humans is believed to be associated with its potentiation of neurotransmitter activity in the CNS. Preclinical studies have shown that venlafaxine and its active metabolite, O-desmethylvenlafaxine (ODV), are potent inhibitors of neuronal serotonin and norepinephrine reuptake and weak inhibitors of dopamine reuptake.

12.2 Pharmacodynamics

Venlafaxine and its active metabolite, O-desmethylvenlafaxine (ODV) have no significant affinity for muscarinic cholinergic, H1-histaminergic, or α1-adrenergic receptors in vitro. Pharmacologic activity at these receptors is hypothesized to be associated with the various anticholinergic, sedative, and cardiovascular effects seen with other psychotropic drugs. Venlafaxine and ODV do not possess monoamine oxidase (MAO) inhibitory activity.

12.3 Pharmacokinetics

Steady-state concentrations of venlafaxine and O-desmethylvenlafaxine (ODV) in plasma are attained within 3 days of oral multiple dose therapy. Venlafaxine and ODV exhibited linear kinetics over the dose range of 75 to 450 mg/day. The mean ± SD apparent elimination half-life for venlafaxine and ODV after administration of 75 mg Venlafaxine Extended Release Tablets under fed conditions were 10.7±3.2 hours and 12.5±3.0 hours respectively. Venlafaxine and ODV are minimally bound at therapeutic concentrations to plasma proteins (27% and 30%, respectively).

Absorption and Distribution

Venlafaxine is well absorbed and extensively metabolized in the liver. ODV is the only major active metabolite. On the basis of mass balance studies, at least 92% of a single oral dose of venlafaxine is absorbed. The absolute bioavailability of venlafaxine is about 45%. Administration of 75 mg Venlafaxine Extended Release Tablets under fed conditions resulted in mean ± SD venlafaxine Cmax of 26.9 ± 13.4 ng/mL and AUC of 1536.3 ± 496.8 ng∙hr/mL. Tmax was 6.3 ± 2.3 hours. ODV mean ± SD Cmax, AUC, Tmax after administration of 75 mg Venlafaxine Extended Release Tablets under fed conditions were 97.9 ± 29.4 ng/mL, 2926.0 ± 746.1 ng∙hr/mL, and 11.6 ± 2.9 hours, respectively.

Administration of venlafaxine hydrochloride extended-release capsules (150 mg q24 hours) generally resulted in lower Cmax (150 ng/mL for venlafaxine and 260 ng/mL for ODV) and later Tmax (5.5 hours for venlafaxine and 9 hours for ODV) than for immediate release venlafaxine tablets (Cmax's for immediate release 75 mg q12 hours were 225 ng/mL for venlafaxine and 290 ng/mL for ODV; Tmax's were 2 hours for venlafaxine and 3 hours for ODV). When equal daily doses of venlafaxine were administered as either an immediate release tablet or the extended-release form of venlafaxine, the exposure to both venlafaxine and ODV would be similar for the two treatments. Venlafaxine Extended Release Tablets would, therefore, provide a slower rate of absorption, but the same extent of absorption compared with the immediate release tablet.

Food did not affect the pharmacokinetic parameters AUC, Cmax, and Tmax of venlafaxine or its active metabolite, ODV, after administration of Venlafaxine Extended Release Tablets. Time of administration (AM vs PM) would not affect the pharmacokinetics of venlafaxine and ODV.

Equal doses of venlafaxine hydrochloride extended-release tablets are bioequivalent to Effexor XR capsules when administered under fed conditions.

Metabolism and Excretion

Following absorption, venlafaxine undergoes extensive presystemic metabolism in the liver, primarily to ODV, but also to N-desmethylvenlafaxine, N,O-didesmethylvenlafaxine, and other minor metabolites. In vitro studies indicate that the formation of ODV is catalyzed by CYP2D6; this has been confirmed in a clinical study showing that patients with low CYP2D6 levels ("poor metabolizers") had increased levels of venlafaxine and reduced levels of ODV compared to people with normal CYP2D6 ("extensive metabolizers"). The differences between the CYP2D6 poor and extensive metabolizers, however, are not expected to be clinically important because the sum of venlafaxine and ODV is similar in the two groups and venlafaxine and ODV are pharmacologically approximately equiactive and equipotent.

Approximately 87% of a venlafaxine dose is recovered in the urine within 48 hours as unchanged venlafaxine (5%), unconjugated ODV (29%), conjugated ODV (26%), or other minor inactive metabolites (27%). Renal elimination of venlafaxine and its metabolites is thus the primary route of excretion.

Special Populations

Age and Gender: A population pharmacokinetic analysis of 404 venlafaxine-treated patients from two studies involving both b.i.d. and t.i.d. regimens showed that dose-normalized trough plasma levels of either venlafaxine or ODV were unaltered by age or gender differences. Dosage adjustment based on the age or gender of a patient is generally not necessary [see Dosage and Administration (2)].

Extensive/Poor Metabolizers: Plasma concentrations of venlafaxine were higher in CYP2D6 poor metabolizers than extensive metabolizers. Because the total exposure (AUC) of venlafaxine and ODV was similar in poor and extensive metabolizer groups, however, there is no need for different venlafaxine dosing regimens for these two groups.

Liver Disease: In 9 subjects with hepatic cirrhosis, the pharmacokinetic disposition of both venlafaxine and ODV was significantly altered after oral administration of venlafaxine. Venlafaxine elimination half-life was prolonged by about 30%, and clearance decreased by about 50% in cirrhotic subjects compared to normal subjects. ODV elimination half-life was prolonged by about 60%, and clearance decreased by about 30% in cirrhotic subjects compared to normal subjects. A large degree of intersubject variability was noted. Three patients with more severe cirrhosis had a more substantial decrease in venlafaxine clearance (about 90%) compared to normal subjects.

In a second study, venlafaxine was administered orally and intravenously in normal (n = 21) subjects, and in Child-Pugh A (n = 8) and Child-Pugh B (n = 11) subjects (mildly and moderately impaired, respectively). Venlafaxine oral bioavailability was increased 2-3 fold, oral elimination half-life was approximately twice as long and oral clearance was reduced by more than half, compared to normal subjects. In hepatically impaired subjects, ODV oral elimination half-life was prolonged by about 40%, while oral clearance for ODV was similar to that for normal subjects. A large degree of intersubject variability was noted.

Dosage adjustment is necessary in these hepatically impaired patients [see Dosage and Administration (2.3) and Use in Specific Populations (8.6)].

Renal Disease: In a renal impairment study, venlafaxine elimination half-life after oral administration was prolonged by about 50% and clearance was reduced by about 24% in renally impaired patients (GFR=10 to 70 mL/min), compared to normal subjects. In dialysis patients, venlafaxine elimination half-life was prolonged by about 180% and clearance was reduced by about 57% compared to normal subjects. Similarly, ODV elimination half-life was prolonged by about 40% although clearance was unchanged in patients with renal impairment (GFR=10 to 70 mL/min) compared to normal subjects. In dialysis patients, ODV elimination half-life was prolonged by about 142% and clearance was reduced by about 56% compared to normal subjects. A large degree of intersubject variability was noted. Dosage adjustment is necessary in these patients [see Dosage and Administration (2.3) and Use in Specific Populations (8.7)].

13 NONCLINICAL TOXICOLOGY

13.1 Carcinogenesis, Mutagenesis, Impairment of Fertility

Carcinogenesis

Venlafaxine was given by oral gavage to mice for 18 months at doses up to 120 mg/kg per day, which was 1.7 times the maximum recommended human dose on a mg/m^2 basis. Venlafaxine was also given to rats by oral gavage for 24 months at doses up to 120 mg/kg per day. In rats receiving the 120 mg/kg dose, plasma concentrations of venlafaxine at necropsy were 1 times (male rats) and 6 times (female rats) the plasma concentrations of patients receiving the maximum recommended human dose. Plasma levels of the O-desmethyl metabolite were lower in rats than in patients receiving the maximum recommended dose. Tumors were not increased by venlafaxine treatment in mice or rats.

Mutagenesis

Venlafaxine and the major human metabolite, O-desmethylvenlafaxine (ODV), were not mutagenic in the Ames reverse mutation assay in Salmonella bacteria or the Chinese hamster ovary/HGPRT mammalian cell forward gene mutation assay. Venlafaxine was also not mutagenic or clastogenic in the in vitro BALB/c-3T3 mouse cell transformation assay, the sister chromatid exchange assay in cultured Chinese hamster ovary cells, or in the in vivo chromosomal aberration assay in rat bone marrow. ODV was not clastogenic in the in vitro Chinese hamster ovary cell chromosomal aberration assay, but elicited a clastogenic response in the in vivo chromosomal aberration assay in rat bone marrow.

Impairment of Fertility

Reproduction and fertility studies in rats showed no effects on male or female fertility at oral doses of up to 2 times the maximum recommended human dose on a mg/m^2 basis.

14 CLINICAL STUDIES

14.1 Major Depressive Disorder

The efficacy of venlafaxine hydrochloride extended-release capsules as a treatment for major depressive disorder was established in two placebo-controlled, short-term, flexible-dose studies in adult outpatients meeting DSM-III-R or DSM-IV criteria for major depressive disorder.

A 12-week study utilizing venlafaxine hydrochloride extended-release capsules doses in a range 75 to 150 mg/day (mean dose for completers was 136 mg/day) and an 8-week study utilizing venlafaxine hydrochloride extended-release capsules doses in a range 75 to 225 mg/day (mean dose for completers was 177 mg/day) both demonstrated superiority of venlafaxine hydrochloride extended-release capsules over placebo on the HAM-D total score, HAM-D Depressed Mood Item, the MADRS total score, the Clinical Global Impressions (CGI) Severity of Illness item, and the CGI Global Improvement item. In both studies, venlafaxine hydrochloride extended-release capsules were also significantly better than placebo for certain factors of the HAM-D, including the anxiety/somatization factor, the cognitive disturbance factor, and the retardation factor, as well as for the psychic anxiety score.

A 4-week study of inpatients meeting DSM-III-R criteria for major depressive disorder with melancholia utilizing venlafaxine hydrochloride immediate-release tablets in a range of 150 to 375 mg/day (t.i.d. schedule) demonstrated superiority of venlafaxine hydrochloride immediate-release tablets over placebo. The mean dose in completers was 350 mg/day.

Examination of gender subsets of the population studied did not reveal any differential responsiveness on the basis of gender.

In one longer-term study, adult outpatients meeting DSM-IV criteria for major depressive disorder who had responded during an 8-week open trial on venlafaxine hydrochloride extended-release capsules (75, 150, or 225 mg, qAM) were randomized to continuation of their same venlafaxine hydrochloride extended-release capsules dose or to placebo, for up to 26 weeks of observation for relapse. Response during the open phase was defined as a CGI Severity of Illness item score of ≤3 and a HAM-D-21 total score of ≤10 at the day 56 evaluation. Relapse during the double-blind phase was defined as follows: (1) a reappearance of major depressive disorder as defined by DSM-IV criteria and a CGI Severity of Illness item score of ≥4 (moderately ill), (2) 2 consecutive CGI Severity of Illness item scores of ≥4, or (3) a final CGI Severity of Illness item score of ≥4 for any patient who withdrew from the study for any reason. Patients receiving continued venlafaxine hydrochloride extended-release capsules treatment experienced significantly lower relapse rates over the subsequent 26 weeks compared with those receiving placebo.

In a second longer-term trial, adult outpatients meeting DSM-III-R criteria for major depressive disorder, recurrent type, who had responded (HAM-D-21 total score ≤12 at the day 56 evaluation) and continued to be improved [defined as the following criteria being met for days 56 through 180: (1) no HAM-D-21 total score ≥20; (2) no more than 2 HAM-D-21 total scores >10, and (3) no single CGI Severity of Illness item score ≥4 (moderately ill)] during an initial 26 weeks of treatment on venlafaxine hydrochloride immediate-release tablets (100 to 200 mg/day, on a b.i.d. schedule) were randomized to continuation of their same dose of venlafaxine hydrochloride immediate-release tablets or to placebo. The follow-up period to observe patients for relapse, defined as a CGI Severity of Illness item score ≥4, was for up to 52 weeks. Patients receiving continued treatment with venlafaxine hydrochloride immediate-release tablets experienced significantly lower relapse rates over the subsequent 52 weeks compared with those receiving placebo.

14.2 Social Anxiety Disorder (Social Phobia)

The efficacy of venlafaxine hydrochloride extended-release capsules as a treatment for Social Anxiety Disorder (also known as Social Phobia) was established in two double-blind, parallel group, 12-week, multicenter, placebo-controlled, flexible-dose studies in adult outpatients meeting DSM-IV criteria for Social Anxiety Disorder. Patients received doses in a range of 75 to 225 mg/day. Efficacy was assessed with the Liebowitz Social Anxiety Scale (LSAS). In these two trials, venlafaxine hydrochloride extended-release capsules were significantly more effective than placebo on change from baseline to endpoint on the LSAS total score.

Examination of subsets of the population studied did not reveal any differential responsiveness on the basis of gender. There was insufficient information to determine the effect of age or race on outcome in these studies.

16 HOW SUPPLIED/STORAGE AND HANDLING

Venlafaxine Extended Release Tablets 37.5 mg are round, biconvex, white coated tablets with OS301 printed on one side. They are supplied as follows:

Unit of Use Bottles of 30 Tablets NDC 0131-3265-32
Unit of Use Bottles of 90 Tablets NDC 0131-3265-46

Venlafaxine Extended Release Tablets 75 mg are round, biconvex, white coated tablets with OS302 printed on one side. They are supplied as follows:

Unit of Use Bottles of 30 Tablets NDC 0131-3266-32
Unit of Use Bottles of 90 Tablets NDC 0131-3266-46

Venlafaxine Extended Release Tablets 150 mg are round, biconvex, white coated tablets with OS303 printed on one side. They are supplied as follows:

Unit of Use Bottles of 30 Tablets NDC 0131-3267-32
Unit of Use Bottles of 90 Tablets NDC 0131-3267-46

Venlafaxine Extended Release Tablets 225 mg are round, biconvex, white coated tablets with OS304 printed on one side. They are supplied as follows:

Unit of Use Bottles of 30 Tablets NDC 0131-3268-32
Unit of Use Bottles of 90 Tablets NDC 0131-3268-46

STORAGE AND HANDLING

Store at 25°C (77°F); excursions permitted to 15-30°C (59-86°F) [see USP Controlled Room Temperature]. Protect from moisture and humidity.

Marketed by:
UPSTATE
PHARMA, LLC
Rochester, NY 14623 USA

For:
Osmotica
Pharmaceutical®
Wilmington, NC 28405, USA

17 PATIENT COUNSELING INFORMATION

See FDA-approved Medication Guide (17.9)

Prescribers or other health professionals should inform patients, their families, and their caregivers about the benefits and risks associated with treatment with Venlafaxine Extended Release Tablets and should counsel them in its appropriate use. A patient Medication Guide about "Antidepressant Medicines, Depression and Other Serious Mental Illness, and Suicidal Thoughts or Actions" is available for Venlafaxine Extended Release Tablets. The prescriber or health professional should instruct patients, their families, and their caregivers to read the Medication Guide and should assist them in understanding its contents. Patients should be given the opportunity to discuss the contents of the Medication Guide and to obtain answers to any questions they may have. The complete text of the Medication Guide is reprinted at the end of this document.

Patients should be advised of the following issues and asked to alert their prescriber if these occur while taking Venlafaxine Extended Release Tablets.

17.1 Clinical Worsening and Suicide Risk

Patients, their families, and their caregivers should be encouraged to be alert to the emergence of anxiety, agitation, panic attacks, insomnia, irritability, hostility, aggressiveness, impulsivity, akathisia (psychomotor restlessness), hypomania, mania, other unusual changes in behavior, worsening of depression, and suicidal ideation, especially early during antidepressant treatment and when the dose is adjusted up or down. Families and caregivers of patients should be advised to look for the emergence of such symptoms on a day-to-day basis, since changes may be abrupt. Such symptoms should be reported to the patient's prescriber or health professional, especially if they are severe, abrupt in onset, or were not part of the patient's presenting symptoms. Symptoms such as these may be associated with an increased risk for suicidal thinking and behavior and indicate a need for very close monitoring and possibly changes in the medication.

17.2 Interference with Cognitive and Motor Performance

Clinical studies were performed to examine the effects of venlafaxine on behavioral performance of healthy individuals. The results revealed no clinically significant impairment of psychomotor, cognitive, or complex behavior performance. However, since any psychoactive drug may impair judgment, thinking, or motor skills, patients should be cautioned about operating hazardous machinery, including automobiles, until they are reasonably certain that venlafaxine therapy does not adversely affect their ability to engage in such activities.

17.3 Concomitant Medication

Patients should be advised to inform their physicians if they are taking, or plan to take, any prescription or over-the-counter drugs, including herbal preparations and nutritional supplements, since there is a potential for interactions. Patients should be cautioned about the risk of serotonin syndrome with the concomitant use of Venlafaxine Extended Release Tablets and triptans, tramadol, tryptophan supplements or other serotonergic agents [see Warnings and Precautions (5.3) and Drug Interactions (7.10)].

Patients should be cautioned about the concomitant use of Venlafaxine Extended Release Tablets and NSAID's, aspirin, warfarin, or other drugs that affect coagulation since combined use of psychotropic drugs that interfere with serotonin reuptake and these agents has been associated with an increased risk of bleeding [see Warnings and Precautions (5.14) and Drug Interactions (7.11)].

17.4 Alcohol

Although venlafaxine has not been shown to increase the impairment of mental and motor skills caused by alcohol, patients should be advised to avoid alcohol while taking venlafaxine.

17.5 Allergic Reactions

Patients should be advised to notify their physician if they develop a rash, hives, or a related allergic phenomenon.

17.6 Pregnancy

Patients should be advised to notify their physician if they become pregnant or intend to become pregnant during therapy.

17.7 Nursing

Patients should be advised to notify their physician if they are breast-feeding an infant.

17.8 Mydriasis

Mydriasis (prolonged dilation of the pupils of the eye) has been reported with venlafaxine. Patients should be advised to notify their physician if they have a history of glaucoma or a history of increased intraocular pressure [see Warnings and Precautions (5.5)].

Medication Guide

Antidepressant Medicines, Depression and Other Serious Mental Illnesses, and Suicidal Thoughts or Actions

Read the Medication Guide that comes with your or your family member's antidepressant medicine. This Medication Guide is only about the risk of suicidal thoughts and actions with antidepressant medicines. Talk to your, or your family member's, healthcare provider about:

- all risks and benefits of treatment with antidepressant medicines
- all treatment choices for depression or other serious mental illness

What is the most important information I should know about antidepressant medicines, depression and other serious mental illnesses, and suicidal thoughts or actions?

1. Antidepressant medicines may increase suicidal thoughts or actions in some children, teenagers, and young adults within the first few months of treatment.

2. Depression and other serious mental illnesses are the most important causes of suicidal thoughts and actions. Some people may have a particularly high risk of having suicidal thoughts or actions. These include people who have (or have a family history of) bipolar illness (also called manic-depressive illness) or suicidal thoughts or actions.

3. How can I watch for and try to prevent suicidal thoughts and actions in myself or a family member?

- Pay close attention to any changes, especially sudden changes, in mood, behaviors, thoughts, or feelings. This is very important when an antidepressant medicine is started or when the dose is changed.
- Call the healthcare provider right away to report new or sudden changes in mood, behavior, thoughts, or feelings.
- Keep all follow-up visits with the healthcare provider as scheduled. Call the healthcare provider between visits as needed, especially if you have concerns about symptoms.

Call a healthcare provider right away if you or your family member has any of the following symptoms, especially if they are new, worse, or worry you:

- thoughts about suicide or dying
- trouble sleeping (insomnia)
- attempts to commit suicide
- new or worse irritability
- new or worse depression
- acting aggressive, being angry, or violent
- new or worse anxiety
- acting on dangerous impulses
- feeling very agitated or restless
- an extreme increase in activity and talking (mania)
- panic attacks
- other unusual changes in behavior or mood

What else do I need to know about antidepressant medicines?

- Never stop an antidepressant medicine without first talking to a healthcare provider.

Stopping an antidepressant medicine suddenly can cause other symptoms.

- Antidepressants are medicines used to treat depression and other illnesses. It is important to discuss all the risks of treating depression and also the risks of not treating it. Patients and their families or other caregivers should discuss all treatment choices with the healthcare provider, not just the use of antidepressants.
- Antidepressant medicines have other side effects. Talk to the healthcare provider about the side effects of the medicine prescribed for you or your family member.
- Antidepressant medicines can interact with other medicines. Know all of the medicines that you or your family member takes. Keep a list of all medicines to show the healthcare provider. Do not start new medicines without first checking with your healthcare provider.
- Not all antidepressant medicines prescribed for children are FDA approved for use in children. Talk to your child's healthcare provider for more information.

Call your doctor for medical advice about side effects. You may report side effects to FDA at 1-800-FDA-1088.

This Medication Guide has been approved by the U.S. Food and Drug Administration for all antidepressants.

Marketed by:
UPSTATE
PHARMA, LLC
Rochester, NY 14623 USA

For:
Osmotica
Pharmaceutical®
Wilmington, NC 28405, USA

Rev. 1E 09/2009